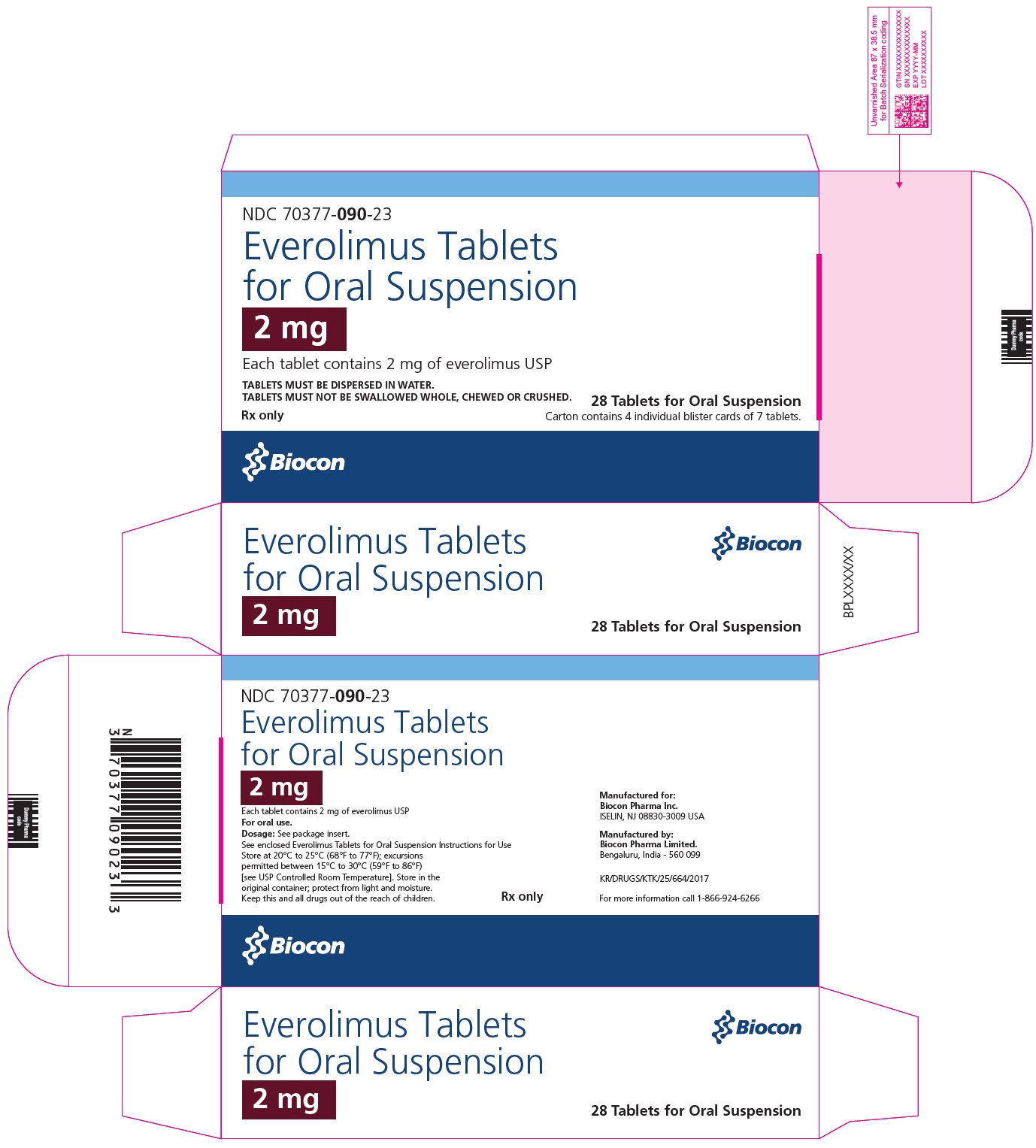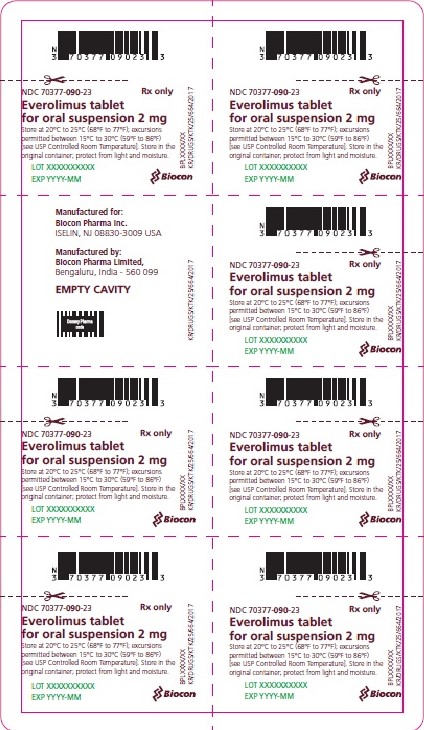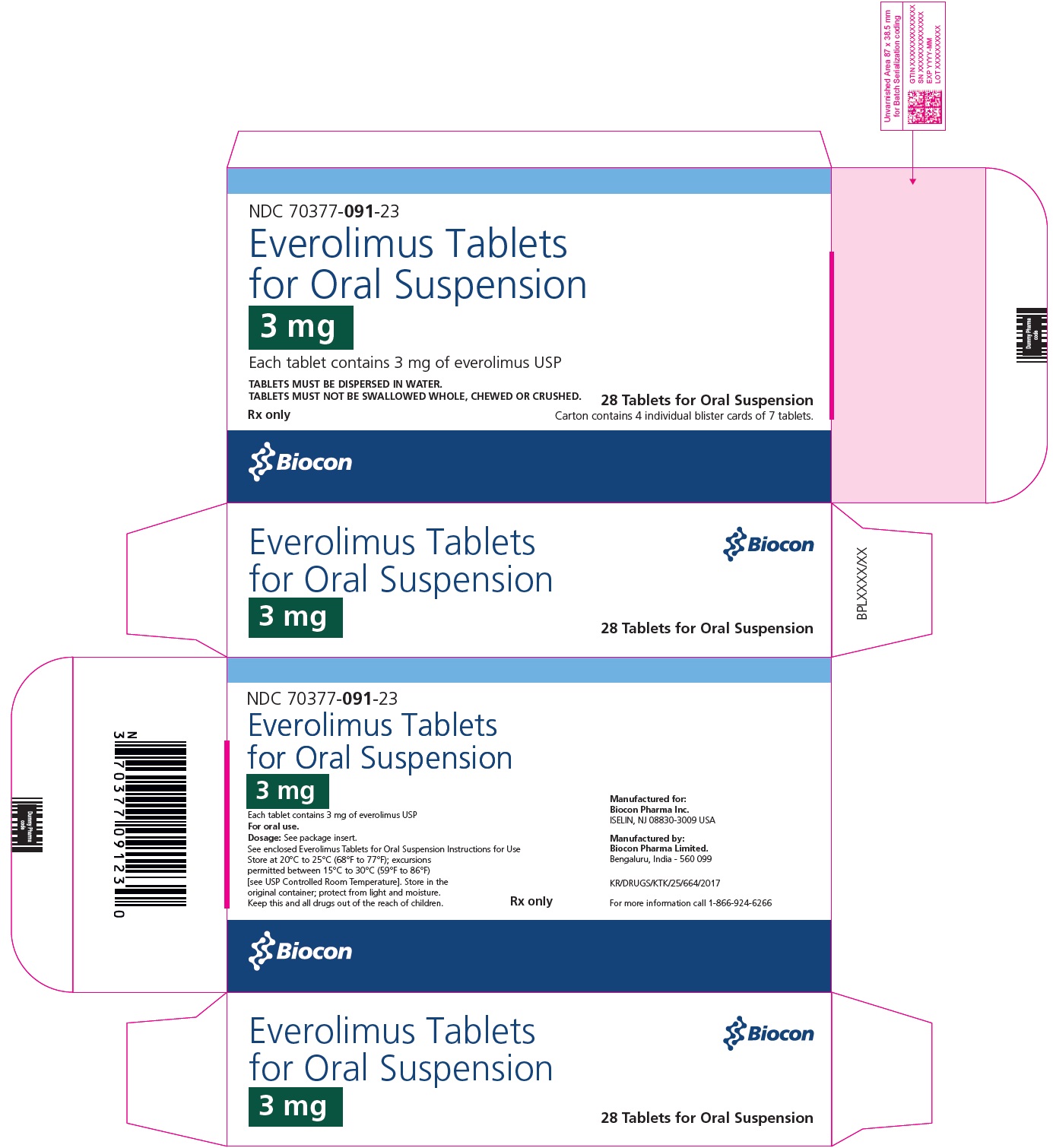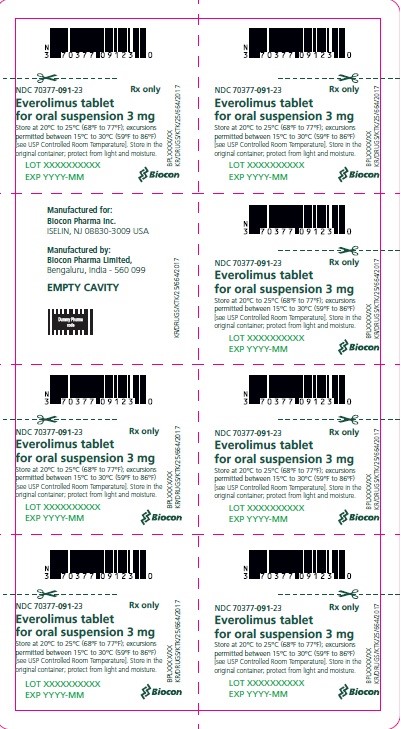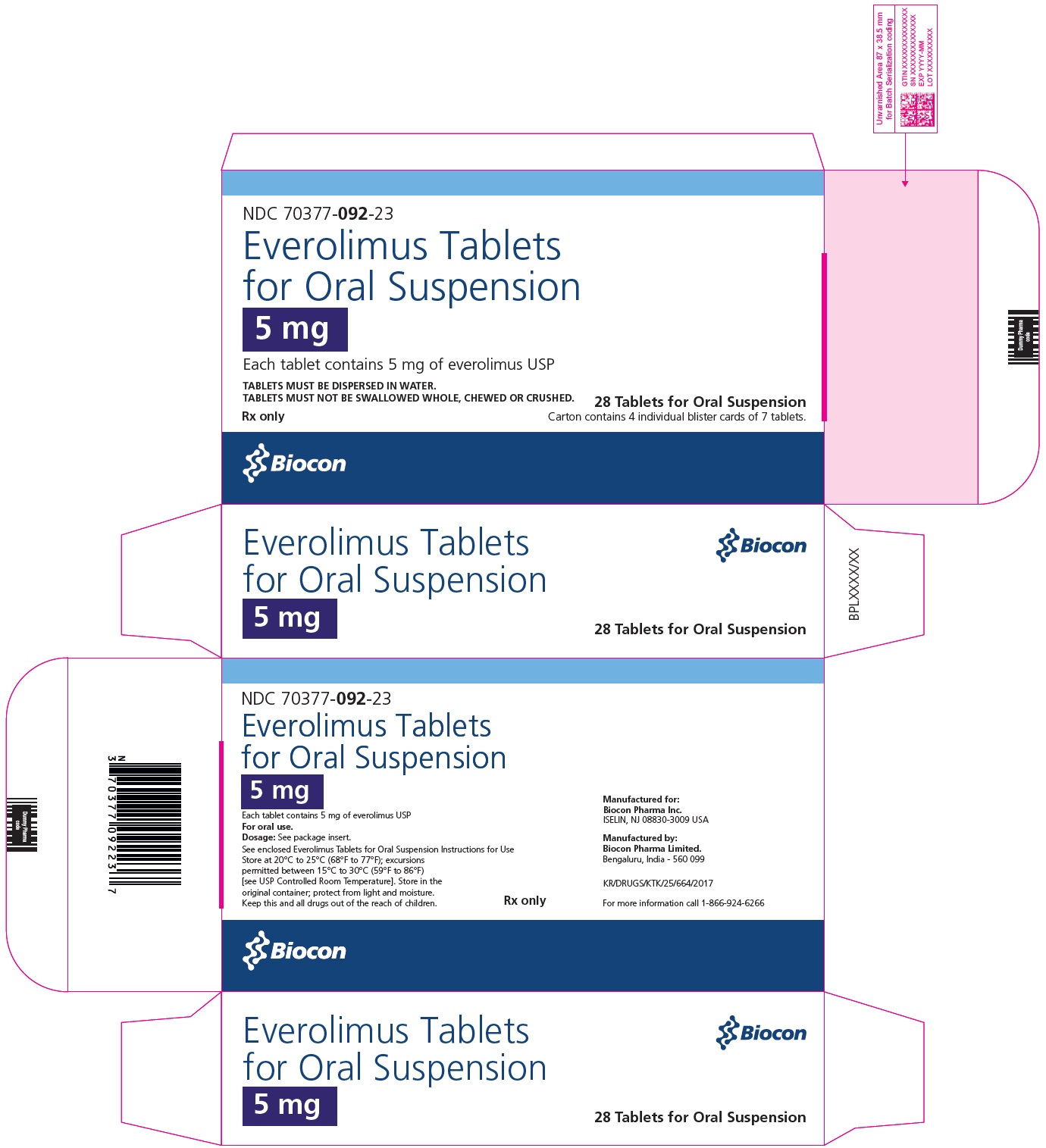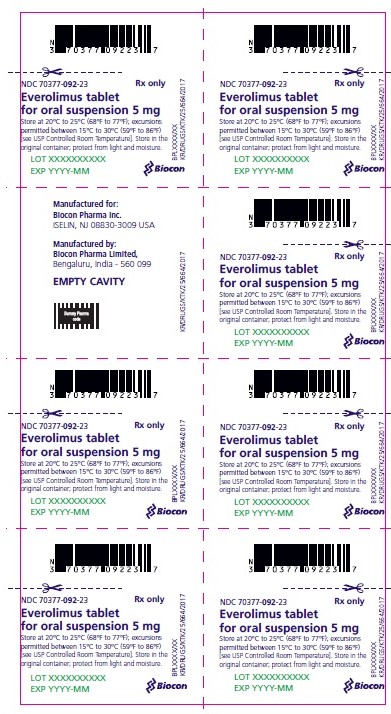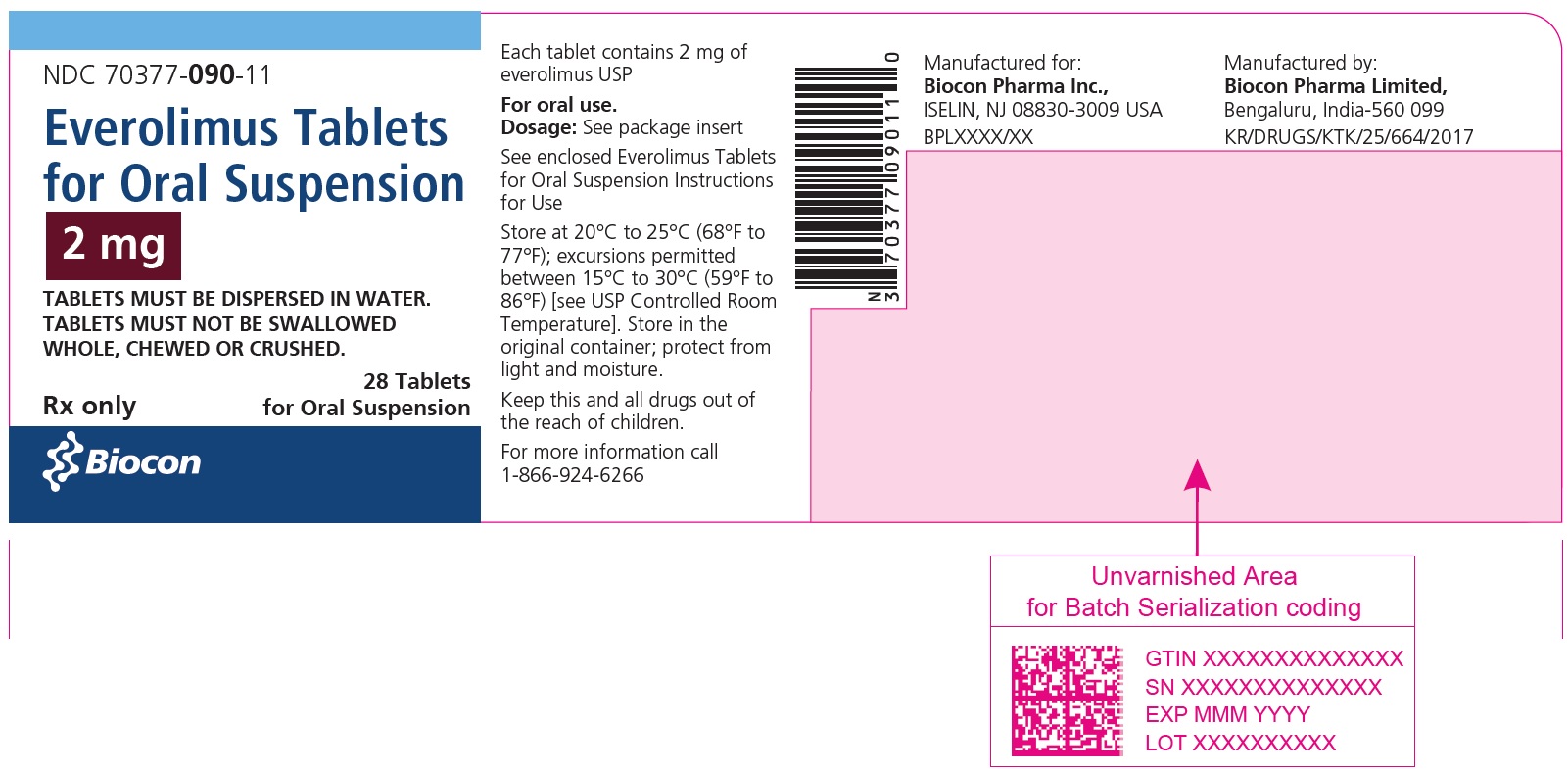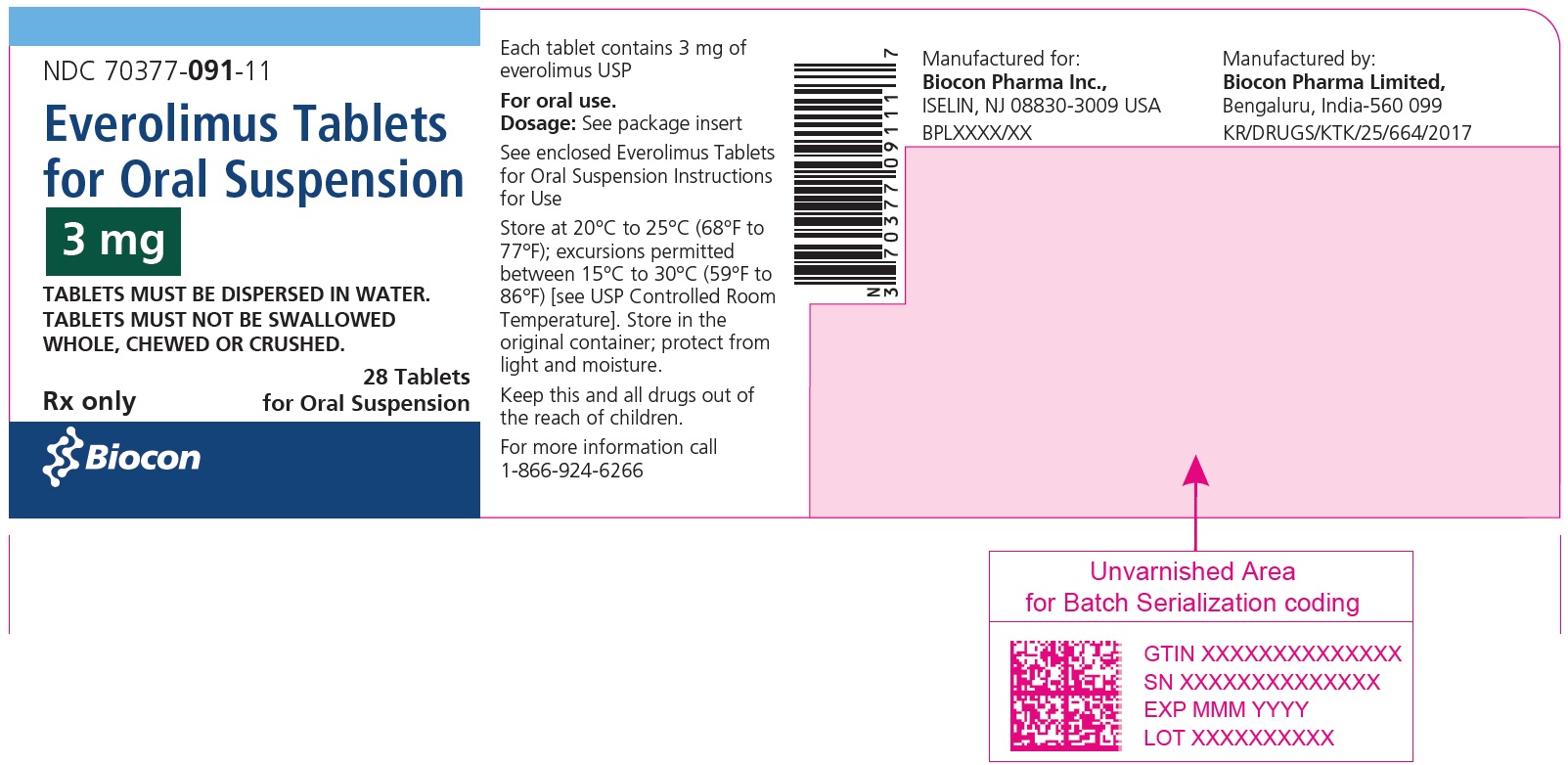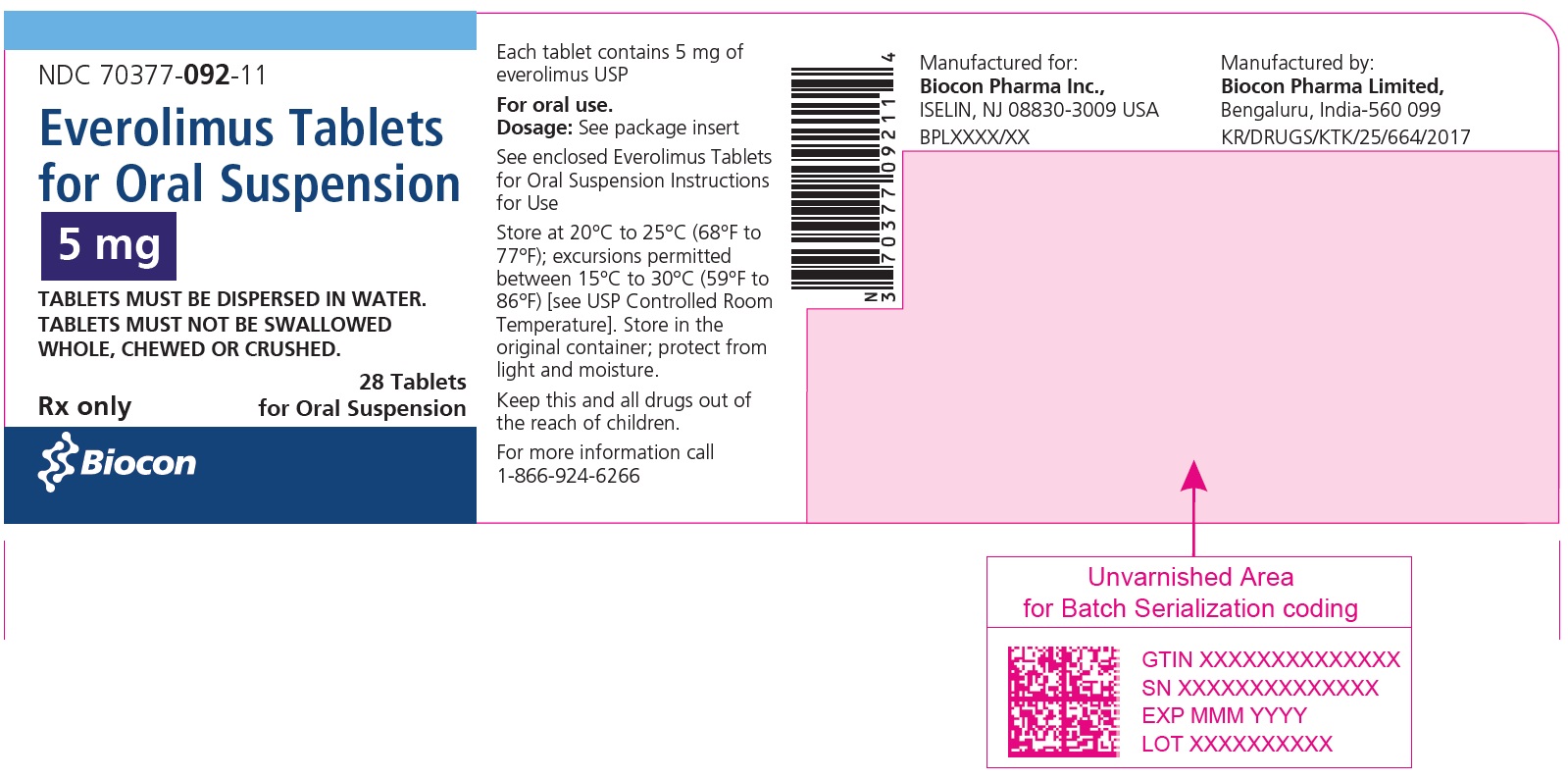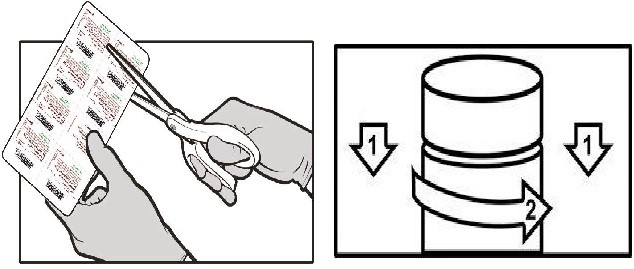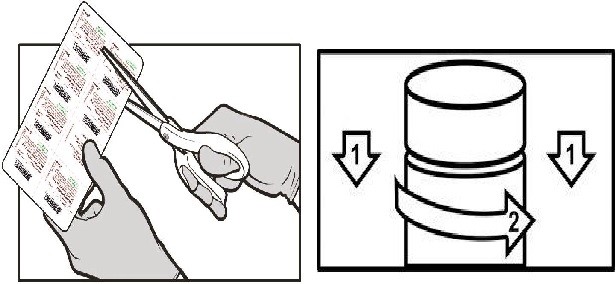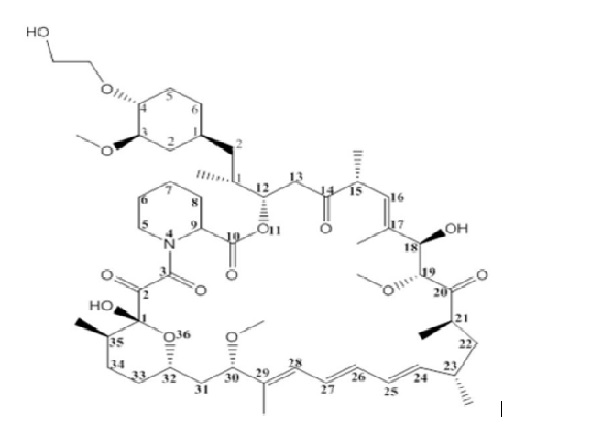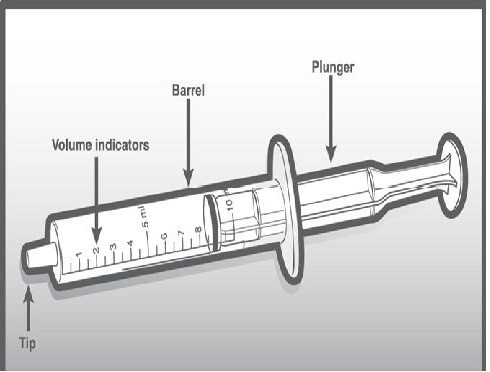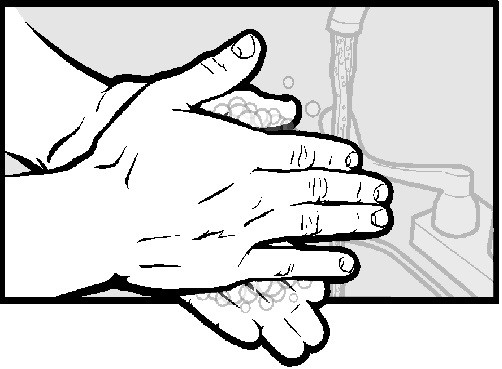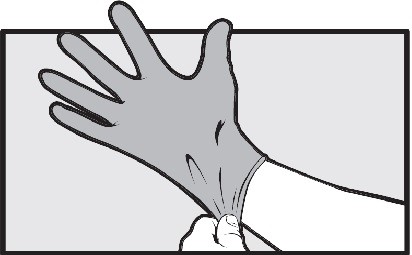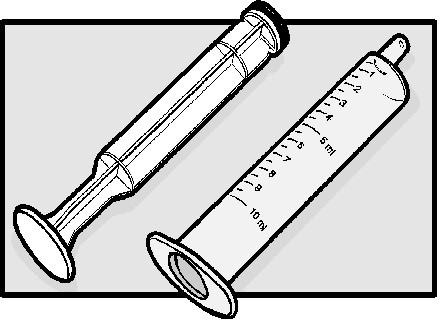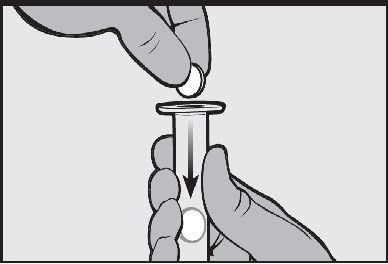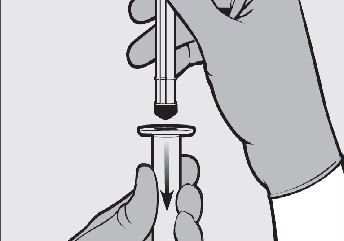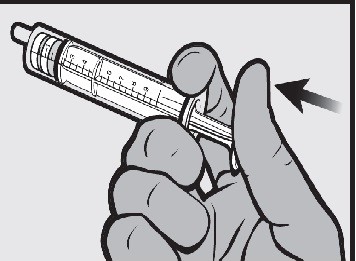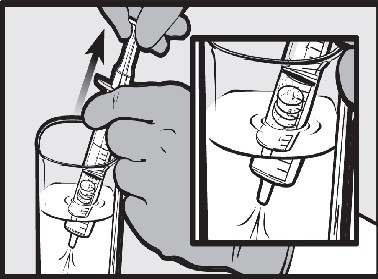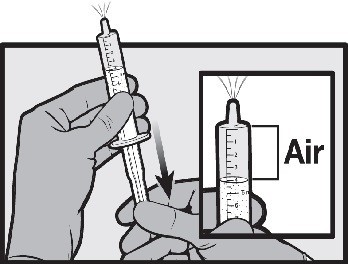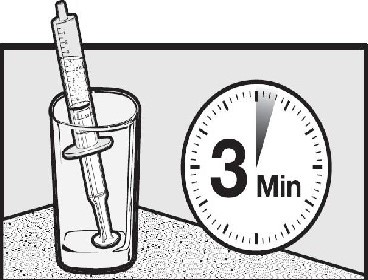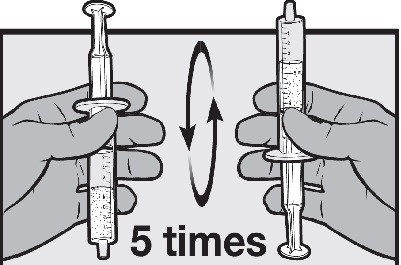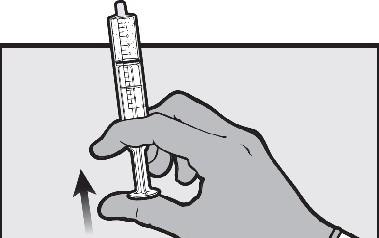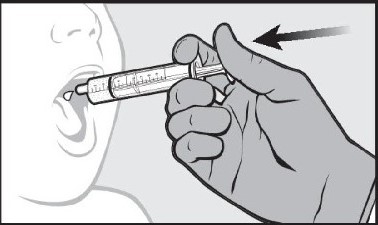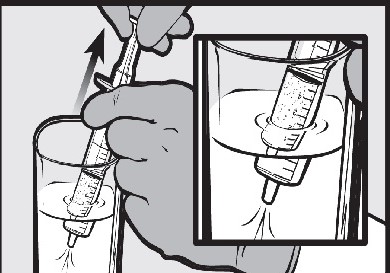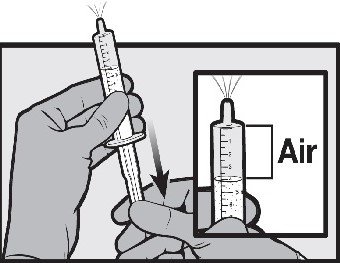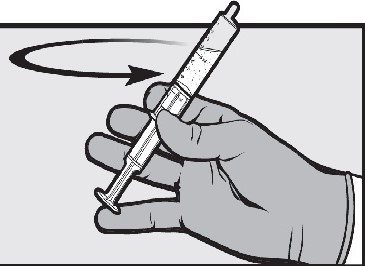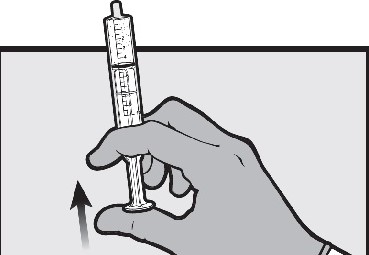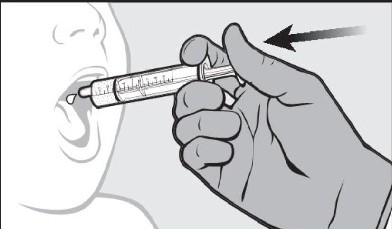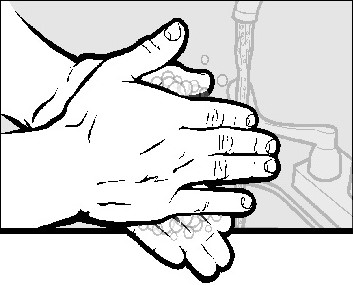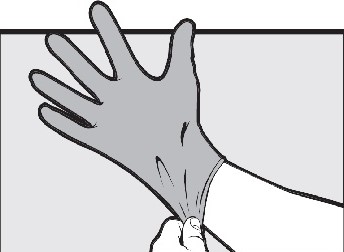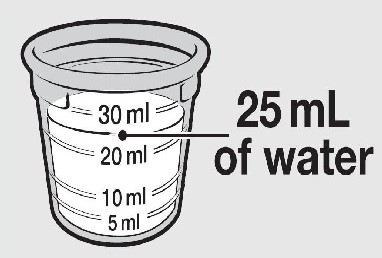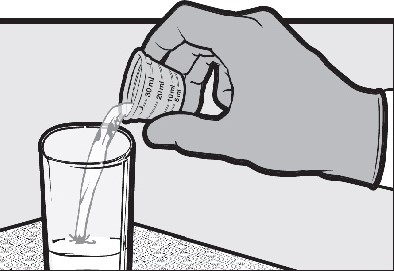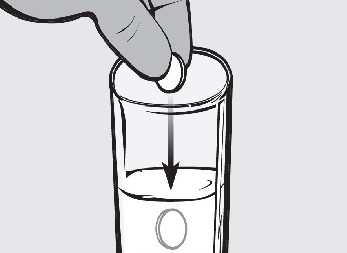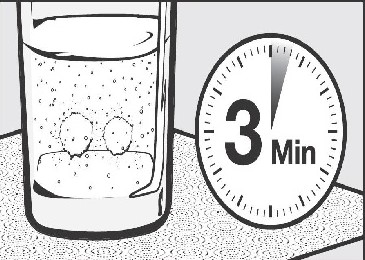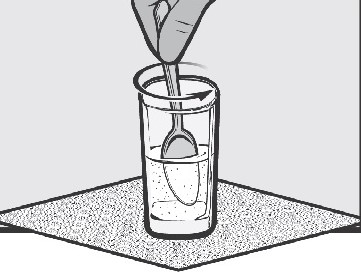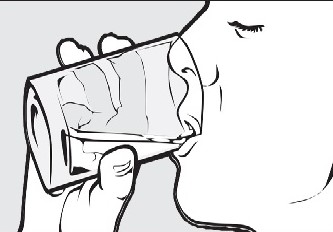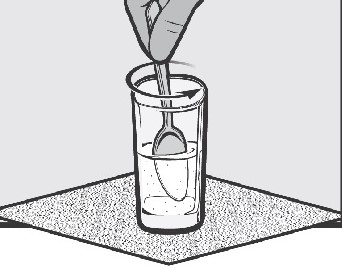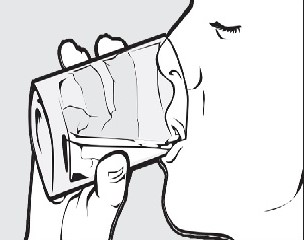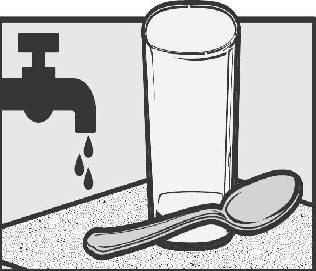 DRUG LABEL: Everolimus
NDC: 70377-090 | Form: TABLET, FOR SUSPENSION
Manufacturer: Biocon Pharma Inc.
Category: prescription | Type: HUMAN PRESCRIPTION DRUG LABEL
Date: 20260114

ACTIVE INGREDIENTS: EVEROLIMUS 2 mg/1 1
INACTIVE INGREDIENTS: BUTYLATED HYDROXYTOLUENE; CROSPOVIDONE; HYPROMELLOSE 2910 (3 MPA.S); MAGNESIUM STEARATE; MANNITOL; MICROCRYSTALLINE CELLULOSE

HIGHLIGHTS OF PRESCRIBING INFORMATION

These highlights do not include all the information needed to use EVEROLIMUS TABLETS FOR ORAL SUSPENSION safely and effectively. See full prescribing information for EVEROLIMUS TABLETS FOR ORAL SUSPENSION.
EVEROLIMUS tablets for oral suspension
Initial U.S. Approval: 2009

1 INDICATIONS AND USAGE

Everolimus tablets for oral suspension are kinase inhibitor indicated for the treatment of adult and pediatric patients aged 1 year and older with TSC who have subependymal giant cell astrocytoma (SEGA) that requires therapeutic intervention but cannot be curatively resected. (1.5)

Everolimus tablets for oral suspension is a kinase inhibitor indicated for the adjunctive treatment of adult and pediatric patients aged 2 years and older with TSC-associated partial-onset seizures. (1.6)

2 DOSAGE AND ADMINISTRATION

Do not combine AFINITOR and everolimus tablets for oral suspension to achieve the total daily dose. (2.1)

Modify the dose for patients with hepatic impairment or for patients taking drugs that inhibit or induce P-glycoprotein (P-gp) and CYP3A4. (2.1)

TSC-Associated SEGA:

- 4.5 mg/m^2 orally once daily; adjust dose to attain trough concentrations of 5-15 ng/mL. (2.6, 2.8)

TSC-Associated Partial-Onset Seizures:

- 5 mg/m^2 orally once daily; adjust dose to attain trough concentrations of 5-15 ng/mL. (2.7, 2.8)

3 DOSAGE FORMS AND STRENGTHS

Everolimus tablets for oral suspension: 2 mg, 3 mg, and 5 mg (3)

4 CONTRAINDICATIONS

Clinically significant hypersensitivity to everolimus or to other rapamycin derivatives. (4)

5 WARNINGS AND PRECAUTIONS

- Non-Infectious Pneumonitis: Monitor for clinical symptoms or radiological changes. Withhold or permanently discontinue based on severity. (2.9, 5.1)
- Infections: Monitor for signs and symptoms of infection. Withhold or permanently discontinue based on severity. (2.9, 5.2)
- Severe Hypersensitivity Reactions: Permanently discontinue for clinically significant hypersensitivity. (5.3)
- Angioedema: Patients taking concomitant angiotensin-converting-enzyme (ACE) inhibitors may be at increased risk for angioedema. Permanently discontinue for angioedema. (5.4, 7.2)
- Stomatitis: Initiate dexamethasone alcohol-free mouthwash when starting treatment. (5.5, 6.1)
- Renal Failure: Monitor renal function prior to treatment and periodically thereafter. (5.6)
- Risk of Impaired Wound Healing: Withhold for at least 1 week prior to elective surgery. Do not administer for at least 2 weeks following major surgery and until adequate wound healing. The safety of resumption of treatment after resolution of wound healing complications has not been established. (5.7)
- Metabolic Disorders: Monitor serum glucose and lipids prior to treatment and periodically thereafter. Withhold or permanently discontinue based on severity. (2.9, 5.9)
- Myelosuppression: Monitor hematologic parameters prior to treatment and periodically thereafter. Withhold or permanently discontinue based on severity. (2.9, 5.10)
- Risk of Infection or Reduced Immune Response with Vaccination: Avoid live vaccines and close contact with those who have received live vaccines. Complete recommended childhood vaccinations prior to starting treatment. (5.11)
- Radiation Sensitization and Radiation Recall: Severe radiation reactions may occur. (5.12, 6.2)
- Embryo-Fetal Toxicity: Can cause fetal harm. Advise patients of reproductive potential of the potential risk to a fetus and to use effective contraception. (5.13, 8.1, 8.3)

6 ADVERSE REACTIONS

- TSC-Associated SEGA: Most common adverse reactions (incidence ≥ 30%) are stomatitis and respiratory tract infection. (6.1)
- TSC-Associated Partial-Onset Seizures: Most common adverse reaction (incidence ≥ 30%) is stomatitis. (6.1)

To report SUSPECTED ADVERSE REACTIONS, contact Biocon Pharma Inc., at 1-866-924-6266 or FDA at 1-800-FDA-1088 or www.fda.gov/medwatch.

7 DRUG INTERACTIONS

- P-gp and strong CYP3A4 inhibitors: Avoid concomitant use. (2.11, 7.1)
- P-gp and moderate CYP3A4 inhibitors: Reduce the dose as recommended. (2.11, 7.1)
- P-gp and strong CYP3A4 inducers: Increase the dose as recommended. (2.12, 7.1)

8 USE IN SPECIFIC POPULATIONS

- For patients with TSC-associated SEGA or TSC-associated partial-onset seizures and severe hepatic impairment, reduce the starting dose and adjust dose to attain target trough concentrations. (2.8, 2.10, 8.6)

FULL PRESCRIBING INFORMATION

1 INDICATIONS AND USAGE

1.5 Tuberous Sclerosis Complex (TSC)-Associated Subependymal Giant Cell Astrocytoma (SEGA)

Everolimus tablets for oral suspension are indicated in adult and pediatric patients aged 1 year and older with TSC for the treatment of SEGA that requires therapeutic intervention but cannot be curatively resected.

1.6 Tuberous Sclerosis Complex (TSC)-Associated Partial-Onset Seizures

Everolimus tablets for oral suspension is indicated for the adjunctive treatment of adult and pediatric patients aged 2 years and older with TSC-associated partial-onset seizures.

2 DOSAGE AND ADMINISTRATION

2.1 Important Dosage Information

- Do not combine AFINITOR and everolimus tablets for oral suspension to achieve the total dose.
- Modify the dosage for patients with hepatic impairment or for patients taking drugs that inhibit or induce P-glycoprotein (P-gp) and CYP3A4 [see Dosage and Administration (2.10, 2.11, 2.12)].

2.6 Recommended Dosage for Tuberous Sclerosis Complex (TSC)-Associated Subependymal Giant Cell Astrocytoma (SEGA)

The recommended starting dosage of everolimus tablets for oral suspension is 4.5 mg/m^2 orally once daily until disease progression or unacceptable toxicity [see Dosage and Administration (2.8)].

2.7 Recommended Dosage for Tuberous Sclerosis Complex (TSC)-Associated Partial-Onset Seizures

The recommended starting dosage of everolimus tablets for oral suspension is 5 mg/m^2 orally once daily until disease progression or unacceptable toxicity [see Dosage and Administration (2.8)].

2.8 Therapeutic Drug Monitoring (TDM) and Dose Titration for Tuberous Sclerosis Complex (TSC)-Associated Subependymal Giant Cell Astrocytoma (SEGA) and TSC-Associated Partial-Onset Seizures

- Monitor everolimus whole blood trough concentrations at time points recommended in Table 1.
- Titrate the dose to attain trough concentrations of 5 ng/mL to 15 ng/mL.
- Adjust the dose using the following equation:
  New dose* = current dose x (target concentration divided by current concentration)
  *The maximum dose increment at any titration must not exceed 5 mg. Multiple dose titrations may be required to attain the target trough concentration.
- When possible, use the same assay and laboratory for TDM throughout treatment.

Table 1: Recommended Timing of Therapeutic Drug Monitoring
Event | When to Assess Trough Concentrations After Event
Initiation of everolimus tablets for oral suspension | 1 to 2 weeks
Modification of everolimus tablets for oral suspension dose | 1 to 2 weeks
Switch between AFINITOR and everolimus tablets for oral suspension | 1 to 2 weeks
Initiation or discontinuation of P-gp and moderate CYP3A4 inhibitor | 2 weeks
Initiation or discontinuation of P-gp and strong CYP3A4 inducer | 2 weeks
Change in hepatic function | 2 weeks
Stable dose with changing body surface area (BSA) | Every 3 to 6 months
Stable dose with stable BSA | Every 6 to 12 months
Abbreviation: P-gp, P-glycoprotein.

2.9 Dosage Modifications for Adverse Reactions

Table 2 summarizes recommendations for dosage modifications of everolimus tablets for oral suspension for the management of adverse reactions.

Table 2: Recommended Dosage Modifications for Everolimus Tablets for Oral Suspension for Adverse Reactions
Adverse Reaction | Severity | Dosage Modification
Non-infectious pneumonitis [see Warnings and Precautions (5.1)] | Grade 2 | Withhold until improvement to Grade 0 or 1. Resume at 50% of previous dose; change to every other day dosing if the reduced dose is lower than the lowest available strength.; Permanently discontinue if toxicity does not resolve or improve to Grade 1 within 4 weeks.
Non-infectious pneumonitis [see Warnings and Precautions (5.1)] | Grade 3 | Withhold until improvement to Grade 0 or 1. Resume at 50% of previous dose; change to every other day dosing if the reduced dose is lower than the lowest available strength.; If toxicity recurs at Grade 3, permanently discontinue.
Non-infectious pneumonitis [see Warnings and Precautions (5.1)] | Grade 4 | Permanently discontinue.
Stomatitis; [see Warnings and Precautions (5.5)] | Grade 2 | Withhold until improvement to Grade 0 or 1. Resume at same dose.; If recurs at Grade 2, withhold until improvement to Grade 0 or 1. Resume at 50% of previous dose; change to every other day dosing if the reduced dose is lower than the lowest available strength.
Stomatitis; [see Warnings and Precautions (5.5)] | Grade 3 | Withhold until improvement to Grade 0 or 1. Resume at 50% of previous dose; change to every other day dosing if the reduced dose is lower than the lowest available strength.
Stomatitis; [see Warnings and Precautions (5.5)] | Grade 4 | Permanently discontinue.
Metabolic events (e.g., hyperglycemia, dyslipidemia) [see Warnings and Precautions (5.9)] | Grade 3 | Withhold until improvement to Grade 0, 1, or 2. Resume at 50% of previous dose; change to every other day dosing if the reduced dose is lower than the lowest available strength.
Metabolic events (e.g., hyperglycemia, dyslipidemia) [see Warnings and Precautions (5.9)] | Grade 4 | Permanently discontinue.
Other non-hematologic toxicities | Grade 2 | If toxicity becomes intolerable, withhold until improvement to Grade 0 or 1. Resume at same dose.; If toxicity recurs at Grade 2, withhold until improvement to Grade 0 or 1. Resume at 50% of previous dose; change to every other day dosing if the reduced dose is lower than the lowest available strength.
Other non-hematologic toxicities | Grade 3 | Withhold until improvement to Grade 0 or 1. Consider resuming at 50% of previous dose; change to every other day dosing if the reduced dose is lower than the lowest available strength.; If recurs at Grade 3, permanently discontinue.
Other non-hematologic toxicities | Grade 4 | Permanently discontinue.
Thrombocytopenia; [see Warnings and Precautions (5.10)] | Grade 2 | Withhold until improvement to Grade 0 or 1. Resume at same dose.
Thrombocytopenia; [see Warnings and Precautions (5.10)] | Grade 3; OR; Grade 4 | Withhold until improvement to Grade 0 or 1. Resume at 50% of previous dose; change to every other day dosing if the reduced dose is lower than the lowest available strength.
Neutropenia; [see Warnings and Precautions (5.10)] | Grade 3 | Withhold until improvement to Grade 0, 1, or 2. Resume at same dose.
Neutropenia; [see Warnings and Precautions (5.10)] | Grade 4 | Withhold until improvement to Grade 0, 1, or 2. Resume at 50% of previous dose; change to every other day dosing if the reduced dose is lower than the lowest available strength.
Febrile neutropenia; [see Warnings and Precautions (5.10)] | Grade 3 | Withhold until improvement to Grade 0, 1, or 2, and no fever. Resume at 50% of previous dose; change to every other day dosing if the reduced dose is lower than the lowest available strength.
Febrile neutropenia; [see Warnings and Precautions (5.10)] | Grade 4 | Permanently discontinue.

2.10 Dosage Modifications for Hepatic Impairment

The recommended dosages of everolimus tablets for oral suspension for patients with hepatic impairment are described in Table 3 [see Use in Specific Populations (8.6)]:

Table 3: Recommended Dosage Modifications for Patients With Hepatic Impairment
Indication | Dose Modification for Everolimus Tablets for Oral Suspension
TSC-Associated SEGA and TSC-Associated Partial-Onset Seizures | - Severe hepatic impairment (Child-Pugh class C) – 2.5 mg/m^2 orally once daily. - Adjust dose based on everolimus trough concentrations as recommended [see Dosage and Administration (2.8)].
Abbreviations: SEGA, Subependymal Giant Cell Astrocytoma; TSC, Tuberous Sclerosis Complex.

2.11 Dosage Modifications for P-gp and CYP3A4 Inhibitors

- Avoid the concomitant use of P-gp and strong CYP3A4 inhibitors [see Drug Interactions (7.1)].
- Avoid ingesting grapefruit and grapefruit juice.
- Reduce the dose for patients taking everolimus tablets for oral suspension with a P-gp and moderate CYP3A4 inhibitor as recommended in Table 4 [see Drug Interactions (7.1), Clinical Pharmacology (12.3)].

Table 4: Recommended Dosage Modifications for Concurrent Use of Everolimus Tablets for Oral Suspension With a P-gp and Moderate CYP3A4 Inhibitor
Indication | Dose Modification for Everolimus Tablets for Oral Suspension
TSC-Associated SEGA and TSC-Associated Partial-Onset Seizures | - Reduce the daily dose by 50%. - Change to every other day dosing if the reduced dose is lower than the lowest available strength. - Resume dose administered prior to inhibitor initiation, once the inhibitor is discontinued for 3 days. - Assess trough concentrations when initiating and discontinuing the inhibitor [see Dosage and Administration (2.8)].

2.12 Dosage Modifications for P-gp and CYP3A4 Inducers

- Avoid concomitant use of St. John’s Wort (Hypericum perforatum).
- Increase the dose for patients taking everolimus tablets for oral suspension with a P-gp and strong CYP3A4 inducer as recommended in Table 5 [see Drug Interactions (7.1), Clinical Pharmacology (12.3)].

Table 5: Recommended Dosage Modifications for Concurrent Use of Everolimus Tablets for Oral Suspension With P-gp and Strong CYP3A4 Inducers
Indication | Dose Modification for Everolimus Tablets for Oral Suspension
TSC-Associated SEGA and TSC-Associated Partial-Onset Seizures | - Double the daily dose using increments of 5 mg or less. Multiple increments may be required. - Addition of another strong CYP3A4 inducer in a patient already receiving treatment with a strong CYP3A4 inducer may not require additional dosage modification. - Assess trough concentrations when initiating and discontinuing the inducer [see Dosage and Administration (2.8)]. - Resume the dose administered before starting any inducer, once all inducers are discontinued for 5 days.

2.13 Administration and Preparation

- Administer everolimus tablets for oral suspension at the same time each day.
- Administer everolimus tablets for oral suspension consistently either with or without food [see Clinical Pharmacology (12.3)].
- If a dose of everolimus tablets for oral suspension is missed, it can be administered up to 6 hours after the time it is normally administered. After more than 6 hours, the dose should be skipped for that day. The next day, everolimus tablets for oral suspension should be administered at its usual time. Double doses should not be administered to make up for the dose that was missed.

Everolimus tablets for oral suspension

- Wear gloves to avoid possible contact with everolimus when preparing suspensions of everolimus tablets for oral suspension for another person.
- Administer as a suspension only.
- Administer suspension immediately after preparation. Discard suspension if not administered within 60 minutes after preparation.
- Prepare suspension in water only.

Using an Oral Syringe to Prepare Oral Suspension:

- Place the prescribed dose into a 10-mL syringe. Do not exceed a total of 10 mg per syringe. If higher doses are required, prepare an additional syringe. Do not break or crush tablets.
- Draw approximately 5 mL of water and 4 mL of air into the syringe.
- Place the filled syringe into a container (tip up) for 3 minutes, until the tablets are in suspension.
- Gently invert the syringe 5 times immediately prior to administration.
- After administration of the prepared suspension, draw approximately 5 mL of water and 4 mL of air into the same syringe, and swirl the contents to suspend remaining particles. Administer the entire contents of the syringe.

Using a Small Drinking Glass to Prepare Oral Suspension:

- Place the prescribed dose into a small drinking glass (maximum size 100 mL) containing approximately 25 mL of water. Do not exceed a total of 10 mg per glass. If higher doses are required, prepare an additional glass. Do not break or crush tablets.
- Allow 3 minutes for suspension to occur.
- Stir the contents gently with a spoon, immediately prior to drinking.
- After administration of the prepared suspension, add 25 mL of water and stir with the same spoon to re-suspend remaining particles. Administer the entire contents of the glass.

3 DOSAGE FORMS AND STRENGTHS

Everolimus tablets for oral suspension

- 2 mg tablets: White to off white, round shaped, flat faced bevelled edged tablets debossed with "E2" on one side and plain on other side and free from physical defects.
- 3 mg tablets: White to off white, round shaped, flat faced bevelled edged tablets debossed with "E3" on one side and plain on other side and free from physical defects.
- 5 mg tablets: White to off white, round shaped, flat faced bevelled edged tablets debossed with "E5" on one side and plain on other side and free from physical defects.

4 CONTRAINDICATIONS

Everolimus tablets for oral suspension are contraindicated in patients with clinically significant hypersensitivity to everolimus or to other rapamycin derivatives [see Warnings and Precautions (5.3)].

5 WARNINGS AND PRECAUTIONS

5.1 Non-infectious Pneumonitis

Non-infectious pneumonitis is a class effect of rapamycin derivatives. Non-infectious pneumonitis was reported in up to 19% of patients treated with everolimus tablets for oral suspension in clinical trials, some cases were reported with pulmonary hypertension (including pulmonary arterial hypertension) as a secondary event. The incidence of Grade 3 and 4 non-infectious pneumonitis was up to 4% and up to 0.2%, respectively [see Adverse Reactions (6.1)]. Fatal outcomes have been observed.

Consider a diagnosis of non-infectious pneumonitis in patients presenting with non-specific respiratory signs and symptoms. Consider opportunistic infections, such as pneumocystis jiroveci pneumonia (PJP) in the differential diagnosis. Advise patients to report promptly any new or worsening respiratory symptoms.

Continue everolimus tablets for oral suspension without dose alteration in patients who develop radiological changes suggestive of non-infectious pneumonitis and have few or no symptoms. Imaging appears to overestimate the incidence of clinical pneumonitis.

For Grade 2 to 4 non-infectious pneumonitis, withhold or permanently discontinue everolimus tablets for oral suspension based on severity [see Dosage and Administration (2.9)]. Corticosteroids may be indicated until clinical symptoms resolve. Administer prophylaxis for PJP when concomitant use of corticosteroids or other immunosuppressive agents are required. The development of pneumonitis has been reported even at a reduced dose.

5.2 Infections

Everolimus tablets for oral suspension has immunosuppressive properties and may predispose patients to bacterial, fungal, viral, or protozoal infections, including infections with opportunistic pathogens [see Adverse Reactions (6.1)]. Localized and systemic infections, including pneumonia, mycobacterial infections, other bacterial infections, invasive fungal infections (e.g., aspergillosis, candidiasis, or PJP), and viral infections (e.g., reactivation of hepatitis B virus) have occurred. Some of these infections have been severe (e.g., sepsis, septic shock, or resulting in multisystem organ failure) or fatal. The incidence of Grade 3 and 4 infections was up to 10% and up to 3%, respectively. The incidence of serious infections was reported at a higher frequency in patients < 6 years of age [see Use in Specific Populations (8.4)].

Complete treatment of preexisting invasive fungal infections prior to starting treatment. Monitor for signs and symptoms of infection. Withhold or permanently discontinue everolimus tablets for oral suspension based on severity of infection [see Dosage and Administration (2.9)].

Administer prophylaxis for PJP when concomitant use of corticosteroids or other immunosuppressive agents are required.

5.3 Severe Hypersensitivity Reactions

Hypersensitivity reactions to everolimus tablets for oral suspension have been observed and include anaphylaxis, dyspnea, flushing, chest pain, and angioedema (e.g., swelling of the airways or tongue, with or without respiratory impairment) [see Contraindications (4)]. The incidence of Grade 3 hypersensitivity reactions was up to 1%. Permanently discontinue everolimus tablets for oral suspension for the development of clinically significant hypersensitivity.

5.4 Angioedema with Concomitant Use of Angiotensin-Converting Enzyme (ACE) Inhibitors

Patients taking concomitant ACE inhibitors with everolimus tablets for oral suspension may be at increased risk for angioedema (e.g., swelling of the airways or tongue, with or without respiratory impairment). In a pooled analysis of randomized double-blind oncology clinical trials, the incidence of angioedema in patients taking AFINITOR with an ACE inhibitor was 6.8% compared to 1.3% in the control arm with an ACE inhibitor. Permanently discontinue everolimus tablets for oral suspension for angioedema.

5.5 Stomatitis

Stomatitis, including mouth ulcers and oral mucositis, has occurred in patients treated with everolimus tablets for oral suspension at an incidence ranging from 44% to 78% across clinical trials. Grades 3-4 stomatitis was reported in 4% to 9% of patients. Stomatitis most often occurs within the first 8 weeks of treatment. When starting everolimus tablets for oral suspension, initiating dexamethasone alcohol-free oral solution as a swish and spit mouthwash reduces the incidence and severity of stomatitis. If stomatitis does occur, mouthwashes and/or other topical treatments are recommended. Avoid alcohol-, hydrogen peroxide-, iodine-, or thyme-containing products, as they may exacerbate the condition. Do not administer antifungal agents, unless fungal infection has been diagnosed.

5.6 Renal Failure

Cases of renal failure (including acute renal failure), some with a fatal outcome, have occurred in patients taking AFINITOR. Elevations of serum creatinine and proteinuria have been reported in patients taking everolimus tablets for oral suspension [see Adverse Reactions (6.1)]. The incidence of Grade 3 and 4 elevations of serum creatinine was up to 2% and up to 1%, respectively. The incidence of Grade 3 and 4 proteinuria was up to 1% and up to 0.5%, respectively. Monitor renal function prior to starting everolimus tablets for oral suspension and annually thereafter. Monitor renal function at least every 6 months in patients who have additional risk factors for renal failure.

5.7 Risk of Impaired Wound Healing

Impaired wound healing can occur in patients who receive drugs that inhibit the VEGF signaling pathway. Therefore, everolimus tablets for oral suspension have the potential to adversely affect wound healing.

Withhold everolimus tablets for oral suspension for at least 1 week prior to elective surgery. Do not administer for at least 2 weeks following major surgery and until adequate wound healing. The safety of resumption of treatment upon resolution of wound healing complications has not been established.

5.9 Metabolic Disorders

Hyperglycemia, hypercholesterolemia, and hypertriglyceridemia have been reported in patients taking everolimus tablets for oral suspension at an incidence up to 75%, 86%, and 73%, respectively. The incidence of these Grade 3 and 4 laboratory abnormalities was up to 15% and up to 0.4%, respectively [see Adverse Reactions (6.1)]. In non-diabetic patients, monitor fasting serum glucose prior to starting everolimus tablets for oral suspension and annually thereafter. In diabetic patients, monitor fasting serum glucose more frequently as clinically indicated. Monitor lipid profile prior to starting everolimus tablets for oral suspension and annually thereafter. When possible, achieve optimal glucose and lipid control prior to starting everolimus tablets for oral suspension. For Grade 3 to 4 metabolic events, withhold or permanently discontinue everolimus tablets for oral suspension based on severity [see Dosage and Administration (2.9)].

5.10 Myelosuppression

Anemia, lymphopenia, neutropenia, and thrombocytopenia have been reported in patients taking everolimus tablets for oral suspension. The incidence of these Grade 3 and 4 laboratory abnormalities was up to 16% and up to 2%, respectively [see Adverse Reactions (6.1)]. Monitor complete blood count (CBC) prior to starting everolimus tablets for oral suspension every 6 months for the first year of treatment and annually thereafter. Withhold or permanently discontinue everolimus tablets for oral suspension based on severity [see Dosage and Administration (2.9)].

5.11 Risk of Infection or Reduced Immune Response With Vaccination

The safety of immunization with live vaccines during everolimus tablets for oral suspension therapy has not been studied. Due to the potential increased risk of infection, avoid the use of live vaccines and close contact with individuals who have received live vaccines during treatment with everolimus tablets for oral suspension. Due to the potential increased risk of infection or reduced immune response with vaccination, complete the recommended childhood series of vaccinations according to American Council on Immunization Practices (ACIP) guidelines prior to the start of therapy. An accelerated vaccination schedule may be appropriate.

5.12 Radiation Sensitization and Radiation Recall

Radiation sensitization and recall, in some cases severe, involving cutaneous and visceral organs (including radiation esophagitis and pneumonitis) have been reported in patients treated with radiation prior to, during, or subsequent to everolimus tablets for oral suspension treatment [see Adverse Reactions (6.2)].

Monitor patients closely when everolimus tablets for oral suspension is administered during or sequentially with radiation treatment.

5.13 Embryo-Fetal Toxicity

Based on animal studies and the mechanism of action, everolimus tablets for oral suspension can cause fetal harm when administered to a pregnant woman. In animal studies, everolimus caused embryo-fetal toxicities in rats when administered during the period of organogenesis at maternal exposures that were lower than human exposures at the clinical dose of 10 mg once daily. Advise pregnant women of the potential risk to a fetus. Advise female patients of reproductive potential to avoid becoming pregnant and to use effective contraception during treatment with everolimus tablets for oral suspension and for 8 weeks after the last dose. Advise male patients with female partners of reproductive potential to use effective contraception during treatment with everolimus tablets for oral suspension and for 4 weeks after the last dose [see Use in Specific Populations (8.1, 8.3)].

6 ADVERSE REACTIONS

The following serious adverse reactions are described elsewhere in the labeling:

- Non-Infectious Pneumonitis [see Warnings and Precautions (5.1)]
- Infections [see Warnings and Precautions (5.2)]
- Severe Hypersensitivity Reactions [see Warnings and Precautions (5.3)]
- Angioedema with Concomitant Use of ACE inhibitors [see Warnings and Precautions (5.4)]
- Stomatitis [see Warnings and Precautions (5.5)]
- Renal Failure [see Warnings and Precautions (5.6)]
- Impaired Wound Healing [see Warnings and Precautions (5.7)]
- Metabolic Disorders [see Warnings and Precautions (5.9)]
- Myelosuppression [see Warnings and Precautions (5.10)]
- Radiation Sensitization and Radiation Recall [see Warnings and Precautions (5.12)]

6.1 Clinical Trials Experience

Because clinical trials are conducted under widely varying conditions, the adverse reaction rates observed cannot be directly compared to rates in other trials and may not reflect the rates observed in clinical practice.

TSC-Associated Subependymal Giant Cell Astrocytoma (SEGA)

The data described below are based on a randomized (2:1), double-blind, placebo-controlled trial (EXIST-1) of AFINITOR in 117 patients with SEGA and TSC. The median age of patients was 9.5 years (0.8 to 26 years), 93% were white, and 57% were male. The median duration of blinded study treatment was 52 weeks (24 to 89 weeks) for patients receiving AFINITOR.

The most common adverse reactions reported for AFINITOR (incidence ≥ 30%) were stomatitis and respiratory tract infection. The most common Grade 3-4 adverse reactions (incidence ≥ 2%) were stomatitis, pyrexia, pneumonia, gastroenteritis, aggression, agitation, and amenorrhea. The most common laboratory abnormalities (incidence ≥ 50%) were hypercholesterolemia and elevated partial thromboplastin time. The most common Grade 3-4 laboratory abnormality (incidence ≥ 3%) was neutropenia.

There were no adverse reactions resulting in permanent discontinuation. Dose adjustments (interruptions or reductions) due to adverse reactions occurred in 55% of AFINITOR-treated patients. The most common adverse reaction leading to AFINITOR dose adjustment was stomatitis.

Adverse reactions reported with an incidence of ≥ 10% for patients receiving AFINITOR and occurring more frequently with AFINITOR than with placebo are reported in Table 16. Laboratory abnormalities are presented in Table 17.

Table 16: Adverse Reactions Reported in ≥ 10% of AFINITOR-Treated Patients With TSC-Associated SEGA in EXIST-1
 | AFINITOR N = 78 |  | Placebo; N = 39
 | All; Grades; % | Grade 3-4; % | All Grades; % | Grade 3-4; %
Gastrointestinal
Stomatitisa | 62 | 9f | 26 | 3f
Vomiting | 22 | 1f | 13 | 0
Diarrhea | 17 | 0 | 5 | 0
Constipation | 10 | 0 | 3 | 0
Infections
Respiratory tract infectionb | 31 | 3 | 23 | 0
Gastroenteritisc | 10 | 5 | 3 | 0
Pharyngitis streptococcal | 10 | 0 | 3 | 0
General
Pyrexia | 23 | 6f | 18 | 3f
Fatigue | 14 | 0 | 3 | 0
Psychiatric
Anxiety, aggression or other behavioral disturbanced | 21 | 5f | 3 | 0
Skin and subcutaneous tissue
Rashe | 21 | 0 | 8 | 0
Acne | 10 | 0 | 5 | 0
Grading according to NCI CTCAE Version 3.0.
aIncludes mouth ulceration, stomatitis, and lip ulceration.
bIncludes respiratory tract infection, upper respiratory tract infection, and respiratory tract infection viral.
cIncludes gastroenteritis, gastroenteritis viral, and gastrointestinal infection.
dIncludes agitation, anxiety, panic attack, aggression, abnormal behavior, and obsessive compulsive disorder.
eIncludes rash, rash generalized, rash macular, rash maculo-papular, rash papular, dermatitis allergic, and urticaria.
fNo Grade 4 adverse reactions were reported.

Amenorrhea occurred in 17% of AFINITOR-treated females aged 10 to 55 years (3 of 18). For this same group of AFINITOR-treated females, the following menstrual abnormalities were reported: dysmenorrhea (6%), menorrhagia (6%), metrorrhagia (6%), and unspecified menstrual irregularity (6%).

The following additional adverse reactions occurred in less than 10% of AFINITOR-treated patients: nausea (8%), pain in extremity (8%), insomnia (6%), pneumonia (6%), epistaxis (5%), hypersensitivity (3%), increased blood luteinizing hormone (LH) levels (1%), and pneumonitis (1%).

Table 17: Selected Laboratory Abnormalities Reported in AFINITOR-Treated Patients With TSC-Associated SEGA in EXIST-1
 | AFINITOR N = 78 |  | Placebo; N = 39
 | All Grades; % | Grade 3-4; % | All Grades; % | Grade 3-4; %
Hematology
Elevated partial thromboplastin time | 72 | 3a | 44 | 5a
Neutropenia | 46 | 9a | 41 | 3a
Anemia | 41 | 0 | 21 | 0
Chemistry
Hypercholesterolemia | 81 | 0 | 39 | 0
Elevated AST | 33 | 0 | 0 | 0
Hypertriglyceridemia | 27 | 0 | 15 | 0
Elevated ALT | 18 | 0 | 3 | 0
Hypophosphatemia | 9 | 1a | 3 | 0
Grading according to NCI CTCAE Version 3.0.
aNo Grade 4 laboratory abnormalities were reported.

Updated safety information from 111 patients treated with AFINITOR for a median duration of 47 months identified the following additional notable adverse reactions and selected laboratory abnormalities: decreased appetite (14%), hyperglycemia (13%), hypertension (11%), urinary tract infection (9%), decreased fibrinogen (8%), cellulitis (6%), abdominal pain (5%), decreased weight (5%), elevated creatinine (5%), and azoospermia (1%).

TSC-Associated Partial-Onset Seizures

The data described below are based on the 18-week Core phase of a randomized, double-blind, multicenter, three-arm trial (EXIST-3) comparing two everolimus trough levels (3-7 ng/mL and 9-15 ng/mL) to placebo as adjunctive antiepileptic therapy in patients with TSC-associated partial-onset seizures. A total of 366 patients were randomized to everolimus tablets for oral suspension low trough (LT) (n = 117), everolimus tablets for oral suspension high trough (HT) (n = 130), or placebo (n = 119). The median age of patients was 10 years (2.2 to 56 years; 28% were < 6 years, 31% were 6 to < 12 years, 22% were 12 to < 18 years, and 18% were ≥ 18 years), 65% were white, and 52% were male. Patients received between one and three concomitant antiepileptic drugs.

The most common adverse reaction reported for everolimus tablets for oral suspension in both arms (incidence ≥ 30%) was stomatitis. The most common Grade 3-4 adverse reactions (incidence ≥ 2%) were stomatitis, pneumonia, and irregular menstruation. The most common laboratory abnormality (incidence ≥ 50%) was hypercholesterolemia. The most common Grade 3-4 laboratory abnormality (incidence ≥ 2%) was neutropenia.

Adverse reactions leading to study drug discontinuation occurred in 5% and 3% of patients in the LT and HT arms, respectively. The most common adverse reaction (incidence ≥ 1%) leading to discontinuation was stomatitis. Dose adjustments (interruptions or reductions) due to adverse reactions occurred in 24% and 35% of patients in the LT and HT arms, respectively. The most common adverse reactions (incidence ≥ 3%) leading to dose adjustments in the everolimus tablets for oral suspension arms were stomatitis, pneumonia, and pyrexia.

Adverse reactions reported with an incidence of ≥ 10% for patients receiving everolimus tablets for oral suspension are presented in Table 18. Laboratory abnormalities are presented in Table 19.

Table 18: Adverse Reactions Reported in ≥ 10% of Everolimus Tablets for Oral Suspension-Treated Patients With TSC-Associated Partial-Onset Seizures in EXIST-3

 | Everolimus Tablets for Oral Suspension |  |  |  |  | Placebo
 |  | Target of; 3-7 ng/mL; N = 117 |  | Target of; 9-15 ng/mL; N = 130 |  | N = 119
 |  | All Grades; % | Grade; 3-4; % | All; Grades; % | Grade; 3-4; % | All; Grades; % | Grade; 3-4; %
 |  | All Grades; % | Grade; 3-4; % | All; Grades; % | Grade; 3-4; % | All; Grades; % | Grade; 3-4; %
Gastrointestinal
Stomatitisa |  | 55 | 3b | 64 | 4b | 9 | 0
Diarrhea |  | 17 | 0 | 22 | 0 | 5 | 0
Vomiting |  | 12 | 0 | 10 | 2b | 9 | 0
Infections
Nasopharyngitis |  | 14 | 0 | 16 | 0 | 16 | 0
Upper respiratory tract infection |  | 13 | 0 | 15 | 0 | 13 | 0.8b
General
Pyrexia |  | 20 | 0 | 14 | 0.8b | 5 | 0
Respiratory, thoracic and mediastinal
Cough |  | 11 | 0 | 10 | 0 | 3 | 0
Skin and subcutaneous tissue
Rash |  | 6 | 0 | 10 | 0 | 3 | 0
Grading according to NCI CTCAE Version 4.03.
aIncludes stomatitis, mouth ulceration, aphthous ulcer, lip ulceration, tongue ulceration, mucosal inflammation, gingival pain.
bNo Grade 4 adverse reactions were reported.

The following additional adverse reactions occurred in < 10% of everolimus tablets for oral suspension treated patients (% everolimus tablets for oral suspension LT, % everolimus tablets for oral suspension HT): decreased appetite (9%, 7%), pneumonia (2%, 4%), aggression (2%, 0.8%), proteinuria (0%, 2%), menorrhagia (0.9%, 0.8%), and pneumonitis (0%, 0.8%).

Table 19: Selected Laboratory Abnormalities Reported in ≥ 10% Everolimus Tablets for Oral Suspension-Treated Patients With TSC-Associated Partial-Onset Seizures

 | Everolimus Tablets for Oral Suspension |  |  |  |  | Placebo
 | Target of; 3-7 ng/mL; N = 117 |  | Target of; 9-15 ng/mL; N = 130 |  | N = 119
 | All Grades; % | Grade; 3-4; % | All; Grades; % | Grade; 3-4; % | All; Grades; % | Grade; 3-4; %
Hematology
Neutropenia | 25 | 4a | 37 | 6 | 23 | 7a
Anemia | 27 | 0.9a | 30 | 0 | 21 | 0.8a
Thrombocytopenia | 12 | 0 | 15 | 0 | 6 | 0
Chemistry
Hypercholesterolemia | 86 | 0 | 85 | 0.8a | 58 | 0
Hypertriglyceridemia | 43 | 2a | 39 | 2 | 22 | 0
Increased ALT | 17 | 0 | 22 | 0 | 6 | 0
Increased AST | 13 | 0 | 19 | 0 | 4 | 0
Hyperglycemia | 19 | 0 | 18 | 0 | 17 | 0
Increased alkaline phosphatase | 24 | 0 | 16 | 0 | 29 | 0
Hypophosphatemia | 9 | 0.9a | 16 | 2 | 3 | 0
Grading according to NCI CTCAE version 4.03.
aNo Grade 4 laboratory abnormalities were reported.

Updated safety information from 357 patients treated with everolimus tablets for oral suspension for a median duration of 48 weeks identified the following additional notable adverse reactions: hypersensitivity (0.6%), angioedema (0.3%), and ovarian cyst (0.3%).

6.2 Postmarketing Experience

The following adverse reactions have been identified during postapproval use of everolimus tablets for oral suspension. Because these reactions are reported voluntarily from a population of uncertain size, it is not always possible to reliably estimate frequency or establish a causal relationship to drug exposure:

- Blood and lymphatic disorders: Thrombotic microangiopathy
- Cardiac: Cardiac failure with some cases reported with pulmonary hypertension (including pulmonary arterial hypertension) as a secondary event
- Gastrointestinal: Acute pancreatitis
- Hepatobiliary: Cholecystitis and cholelithiasis
- Infections: Sepsis and septic shock
- Nervous system: Reflex sympathetic dystrophy
- Vascular: Arterial thrombotic events, lymphedema
- Injury, poisoning and procedural complications: Radiation Sensitization and Radiation Recall

7 DRUG INTERACTIONS

7.1 Effect of Other Drugs on Everolimus Tablets for Oral Suspension

Inhibitors

Avoid the concomitant use of P-gp and strong CYP3A4 inhibitors [see Dosage and Administration (2.11), Clinical Pharmacology (12.3)].

Reduce the dose for patients taking everolimus tablets for oral suspension with a P-gp and moderate CYP3A4 inhibitor as recommended [see Dosage and Administration (2.11), Clinical Pharmacology (12.3)].

Inducers

Increase the dose for patients taking everolimus tablets for oral suspension with a P-gp and strong CYP3A4 inducer as recommended [see Dosage and Administration (2.12), Clinical Pharmacology (12.3)].

7.2 Effects of Combination Use of Angiotensin Converting Enzyme (ACE) Inhibitors

Patients taking concomitant ACE inhibitors with everolimus tablets for oral suspension may be at increased risk for angioedema. Avoid the concomitant use of ACE inhibitors with everolimus tablets for oral suspension [see Warnings and Precautions (5.4)].

8 USE IN SPECIFIC POPULATIONS

8.1 Pregnancy

Risk Summary

Based on animal studies and the mechanism of action [see Clinical Pharmacology (12.1)], everolimus tablets for oral suspension can cause fetal harm when administered to a pregnant woman. There are limited case reports of AFINITOR use in pregnant women; however, these reports are not sufficient to inform about risks of birth defects or miscarriage. In animal studies, everolimus caused embryo-fetal toxicities in rats when administered during the period of organogenesis at maternal exposures that were lower than human exposures at the recommended dose of AFINITOR 10 mg orally once daily (see Data). Advise pregnant women of the potential risk to the fetus.

In the U.S. general population, the estimated background risk of major birth defects and miscarriage is 2% to 4% and 15% to 20% of clinically recognized pregnancies, respectively.

Data

Animal Data

In animal reproductive studies, oral administration of everolimus to female rats before mating and through organogenesis induced embryo-fetal toxicities, including increased resorption, pre-implantation and post-implantation loss, decreased numbers of live fetuses, malformation (e.g., sternal cleft), and retarded skeletal development. These effects occurred in the absence of maternal toxicities. Embryo-fetal toxicities in rats occurred at doses ≥ 0.1 mg/kg (0.6 mg/m^2) with resulting exposures of approximately 4% of the human exposure at the recommended dose of AFINITOR 10 mg orally once daily based on area under the curve (AUC). In rabbits, embryo-toxicity evident as an increase in resorptions occurred at an oral dose of 0.8 mg/kg (9.6 mg/m^2), approximately 1.6 times the recommended dose of AFINITOR 10 mg orally once daily or the median dose administered to patients with tuberous sclerosis complex (TSC)-associated subependymal giant cell astrocytoma (SEGA), and 1.3 times the median dose administered to patients with TSC-associated partial-onset seizures based on BSA. The effect in rabbits occurred in the presence of maternal toxicities.

In a pre- and post-natal development study in rats, animals were dosed from implantation through lactation. At the dose of 0.1 mg/kg (0.6 mg/m^2), there were no adverse effects on delivery and lactation or signs of maternal toxicity; however, there were reductions in body weight (up to 9% reduction from the control) and in survival of offspring (~5% died or missing). There were no drug-related effects on the developmental parameters (morphological development, motor activity, learning, or fertility assessment) in the offspring.

8.2 Lactation

Risk Summary

There are no data on the presence of everolimus or its metabolites in human milk, the effects of everolimus on the breastfed infant or on milk production. Everolimus and its metabolites passed into the milk of lactating rats at a concentration 3.5 times higher than in maternal serum. Because of the potential for serious adverse reactions in breastfed infants from everolimus, advise women not to breastfeed during treatment with everolimus tablets for oral suspension and for 2 weeks after the last dose.

8.3 Females and Males of Reproductive Potential

Pregnancy Testing

Verify the pregnancy status of females of reproductive potential prior to starting everolimus tablets for oral suspension [see Use in Specific Populations (8.1)].

Contraception

Everolimus tablets for oral suspension can cause fetal harm when administered to pregnant women [see Use in Specific Populations (8.1)].

Females: Advise female patients of reproductive potential to use effective contraception during treatment with everolimus tablets for oral suspension and for 8 weeks after the last dose.

Males: Advise male patients with female partners of reproductive potential to use effective contraception during treatment with everolimus tablets for oral suspension and for 4 weeks after the last dose.

Infertility

Females: Menstrual irregularities, secondary amenorrhea, and increases in luteinizing hormone (LH) and follicle stimulating hormone (FSH) occurred in female patients taking everolimus tablets for oral suspension. Based on these findings, everolimus tablets for oral suspension may impair fertility in female patients [see Adverse Reactions (6.1), Nonclinical Toxicology (13.1)].

Males: Cases of reversible azoospermia have been reported in male patients taking AFINITOR. In male rats, sperm motility, sperm count, plasma testosterone levels and fertility were diminished at AUC similar to those of the clinical dose of AFINITOR 10 mg orally once daily. Based on these findings, everolimus tablets for oral suspension may impair fertility in male patients [see Nonclinical Toxicology (13.1)].

8.4 Pediatric Use

TSC-Associated SEGA

The safety and effectiveness of everolimus tablets for oral suspension have been established in pediatric patients age 1 year and older with TSC-associated SEGA that requires therapeutic intervention but cannot be curatively resected. Use of everolimus tablets for oral suspension for this indication is supported by evidence from a randomized, double-blind, placebo-controlled trial in adult and pediatric patients (EXIST-1); an open-label, single-arm trial in adult and pediatric patients (Study 2485); and additional pharmacokinetic data in pediatric patients [see Adverse Reactions (6.1), Clinical Pharmacology (12.3), Clinical Studies (14.5)]. The safety and effectiveness of everolimus tablets for oral suspension have not been established in pediatric patients less than 1 year of age with TSC-associated SEGA.

In EXIST-1, the incidence of infections and serious infections were reported at a higher frequency in patients < 6 years of age. Ninety-six percent of 23 AFINITOR-treated patients < 6 years had at least one infection compared to 67% of 55 AFINITOR-treated patients ≥ 6 years. Thirty-five percent of 23 AFINITOR-treated patients < 6 years of age had at least 1 serious infection compared to 7% of 55 AFINITOR-treated patients ≥ 6 years.

Although a conclusive determination cannot be made due to the limited number of patients and lack of a comparator arm in the open label follow-up periods of EXIST-1 and Study 2485, AFINITOR did not appear to adversely impact growth and pubertal development in the 115 pediatric patients treated with AFINITOR for a median duration of 4.1 years.

TSC-Associated Partial-Onset Seizures

The safety and effectiveness of everolimus tablets for oral suspension has been established for the adjunctive treatment of pediatric patients aged 2 years and older with TSC-associated partial-onset seizures. Use of everolimus tablets for oral suspension for this indication is supported by evidence from a randomized, double-blind, placebo-controlled trial in adult and pediatric patients (EXIST-3) with additional pharmacokinetic data in pediatric patients [see Adverse Reactions (6.1), Clinical Pharmacology (12.3), Clinical Studies (14.6)]. The safety and effectiveness of everolimus tablets for oral suspension and AFINITOR have not been established for the adjunctive treatment of pediatric patients less than 2 years of age with TSC-associated partial-onset seizures.

The incidence of infections and serious infections were reported at a higher frequency in patients < 6 years of age compared to patients ≥ 6 years old. Seventy-seven percent of 70 everolimus tablets for oral suspension-treated patients < 6 years had at least one infection, compared to 53% of 177 everolimus tablets for oral suspension-treated patients ≥ 6 years. Sixteen percent of 70 everolimus tablets for oral suspension-treated patients < 6 years of age had at least 1 serious infection, compared to 4% of 177 everolimus tablets for oral suspension-treated patients ≥ 6 years of age. Two fatal cases due to infections were reported in pediatric patients.

8.6 Hepatic Impairment

Everolimus tablets for oral suspension exposure may increase in patients with hepatic impairment [see Clinical Pharmacology (12.3)].

For patients with TSC-associated SEGA and TSC-associated partial-onset seizures who have severe hepatic impairment (Child-Pugh class C), reduce the starting dose of everolimus tablets for oral suspension as recommended and adjust the dose based on everolimus trough concentrations [see Dosage and Administration (2.8, 2.10)].

11 DESCRIPTION

Everolimus tablets for oral suspension are kinase inhibitor.

The chemical name of everolimus USP is (1R,9S,12S,15R,16E,18R,19R,21R,23S,24E,26E,28E,30S,32S,35R)-1,18- dihydroxy-12-{(1R)-2-[(1S,3R,4R)-4-(2-hydroxyethoxy)-3-methoxycyclohexyl]-1-methylethyl}-19,30-dimethoxy-15,17,21,23,29,35-hexamethyl-11,36-dioxa-4-aza-tricyclo[30.3.1.0^4,9]hexatriaconta-16,24,26,28-tetraene-2,3,10,14,20-pentaone. The molecular formula is C53H83NO14 and the molecular weight is 958.2 g/mol. The structural formula is:

Everolimus tablets for oral suspension for oral administration contains 2 mg, 3 mg or 5 mg of everolimus, USP and the following inactive ingredients: butylated hydroxytoluene, colloidal silicon dioxide, crospovidone, hypromellose, magnesium stearate, mannitol, and microcrystalline cellulose.

12 CLINICAL PHARMACOLOGY

12.1 Mechanism of Action

Everolimus is an inhibitor of mammalian target of rapamycin (mTOR), a serine-threonine kinase, downstream of the PI3K/AKT pathway. The mTOR pathway is dysregulated in several human cancers and in tuberous sclerosis complex (TSC). Everolimus binds to an intracellular protein, FKBP-12, resulting in an inhibitory complex formation with mTOR complex 1 (mTORC1) and thus inhibition of mTOR kinase activity. Everolimus reduced the activity of S6 ribosomal protein kinase (S6K1) and eukaryotic initiation factor 4E-binding protein (4E-BP1), downstream effectors of mTOR, involved in protein synthesis. S6K1 is a substrate of mTORC1 and phosphorylates the activation domain 1 of the estrogen receptor which results in ligand-independent activation of the receptor. In addition, everolimus inhibited the expression of hypoxia-inducible factor (e.g., HIF-1) and reduced the expression of vascular endothelial growth factor (VEGF). Inhibition of mTOR by everolimus has been shown to reduce cell proliferation, angiogenesis, and glucose uptake in in vitro and/or in vivo studies.

Two regulators of mTORC1 signaling are the oncogene suppressors tuberin-sclerosis complexes 1 and 2 (TSC1, TSC2). Loss or inactivation of either TSC1 or TSC2 leads to activation of downstream signaling. In TSC, a genetic disorder, inactivating mutations in either the TSC1 or the TSC2 gene lead to hamartoma formation throughout the body as well as seizures and epileptogenesis. Overactivation of mTOR results in neuronal dysplasia, aberrant axonogenesis and dendrite formation, increased excitatory synaptic currents, reduced myelination, and disruption of the cortical laminar structure causing abnormalities in neuronal development and function. Treatment with an mTOR inhibitor in animal models of mTOR dysregulation in the brain resulted in seizure suppression, prevention of the development of new-onset seizures, and prevention of premature death.

12.2 Pharmacodynamics

Exposure-Response Relationship

In patients with TSC-associated subependymal giant cell astrocytoma (SEGA), the magnitude of the reduction in SEGA volume was correlated with the everolimus trough concentration.

In patients with TSC-associated partial-onset seizures, the magnitude of the reduction in absolute seizure frequency was correlated with the everolimus trough concentration.

Cardiac Electrophysiology

In a randomized, placebo-controlled, cross-over study, 59 healthy subjects were administered a single oral dose of AFINITOR (20 mg and 50 mg) and placebo. AFINITOR at single doses up to 50 mg did not prolong the QT/QTc interval.

12.3 Pharmacokinetics

Absorption

In patients with TSC-associated SEGA, everolimus Cmin was approximately dose-proportional within the dose range from 1.35 mg/m^2 to 14.4 mg/m^2.

Effect of Food: In healthy subjects who received 9 mg of everolimus tablets for oral suspension, high-fat meals (containing approximately 1000 calories and 55 grams of fat) reduced everolimus AUC by 12% and Cmax by 60% and low-fat meals (containing approximately 500 calories and 20 grams of fat) reduced everolimus AUC by 30% and Cmax by 50%.

Relative Bioavailability: The AUCinf of everolimus was equivalent between everolimus tablets for oral suspension and AFINITOR; the Cmax of everolimus in the everolimus tablets for oral suspension dosage form was 20% to 36% lower than that of AFINITOR. The predicted trough concentrations at steady-state were similar after daily administration.

Distribution

The blood-to-plasma ratio of everolimus, which is concentration-dependent over the range of 5 to 5000 ng/mL, is 17% to 73%. The amount of everolimus confined to the plasma is approximately 20% at blood concentrations observed in cancer patients given AFINITOR 10 mg orally once daily. Plasma protein binding is approximately 74% both in healthy subjects and in patients with moderate hepatic impairment.

Elimination

The mean elimination half-life of everolimus is approximately 30 hours.

Metabolism: Everolimus is a substrate of CYP3A4. Following oral administration, everolimus is the main circulating component in human blood. Six main metabolites of everolimus have been detected in human blood, including three monohydroxylated metabolites, two hydrolytic ring-opened products, and a phosphatidylcholine conjugate of everolimus. These metabolites were also identified in animal species used in toxicity studies, and showed approximately 100-times less activity than everolimus itself.

Excretion: No specific elimination studies have been undertaken in cancer patients. Following the administration of a 3 mg single dose of radiolabeled everolimus in patients who were receiving cyclosporine, 80% of the radioactivity was recovered from the feces, while 5% was excreted in the urine. The parent substance was not detected in urine or feces.

Specific Populations

No relationship was apparent between oral clearance and age or sex in patients with cancer.

Patients with Renal Impairment: No significant influence of creatinine clearance (25 to 178 mL/min) was detected on oral clearance (CL/F) of everolimus.

Patients with Hepatic Impairment: Compared to normal subjects, there was a 1.8-fold, 3.2-fold, and 3.6-fold increase in AUC for subjects with mild (Child-Pugh class A), moderate (Child-Pugh class B), and severe (Child-Pugh class C) hepatic impairment, respectively. In another study, the average AUC of everolimus in subjects with moderate hepatic impairment (Child-Pugh class B) was twice that found in subjects with normal hepatic function [see Dosage and Administration (2.10), Use in Specific Populations (8.6)].

Pediatric Patients: In patients with TSC-associated SEGA or TSC-associated partial-onset seizures, the mean Cmin values normalized to mg/m^2 dose in pediatric patients (< 18 years of age) were lower than those observed in adults, suggesting that everolimus clearance adjusted to BSA was higher in pediatric patients as compared to adults.

Race or Ethnicity: Based on a cross-study comparison, Japanese patients had on average exposures that were higher than non-Japanese patients receiving the same dose. Oral clearance (CL/F) is on average 20% higher in black patients than in white patients.

Drug Interaction Studies

Effect of CYP3A4 and P-glycoprotein (P-gp) Inhibitors on Everolimus: Everolimus exposure increased when AFINITOR was coadministered with:

- ketoconazole (a P-gp and strong CYP3A4 inhibitor) - Cmax and AUC increased by 3.9- and 15-fold, respectively.
- erythromycin (a P-gp and moderate CYP3A4 inhibitor) - Cmax and AUC increased by 2- and 4.4-fold, respectively.
- verapamil (a P-gp and moderate CYP3A4 inhibitor) - Cmax and AUC increased by 2.3- and 3.5-fold, respectively.

Effect of CYP3A4 and P-gp Inducers on Everolimus: The coadministration of AFINITOR with rifampin, a P-gp and strong inducer of CYP3A4, decreased everolimus AUC by 63% and Cmax by 58% compared to AFINITOR alone [see Dosage and Administration (2.12)].

Effect of Everolimus on CYP3A4 Substrates: No clinically significant pharmacokinetic interactions were observed between AFINITOR and the HMG-CoA reductase inhibitors atorvastatin (a CYP3A4 substrate), pravastatin (a non CYP3A4-substrate), and simvastatin (a CYP3A4 substrate).

The coadministration of an oral dose of midazolam (sensitive CYP3A4 substrate) with AFINITOR resulted in a 25% increase in midazolam Cmax and a 30% increase in midazolam AUC0-inf.

Effect of Everolimus on Antiepileptic Drugs (AEDs): Everolimus increased pre-dose concentrations of the carbamazepine, clobazam, oxcarbazepine, and clobazam’s metabolite N-desmethylclobazam by about 10%. Everolimus had no impact on pre-dose concentrations of AEDs that are substrates of CYP3A4 (e.g., clonazepam and zonisamide) or other AEDs, including valproic acid, topiramate, phenobarbital, and phenytoin.

13 NONCLINICAL TOXICOLOGY

13.1 Carcinogenesis, Mutagenesis, Impairment of Fertility

Administration of everolimus for up to 2 years did not indicate oncogenic potential in mice and rats up to the highest doses tested (0.9 mg/kg) corresponding, respectively to 3.9 and 0.2 times the estimated human exposure based on AUC at the recommended dose of AFINITOR 10 mg orally once daily.

Everolimus was not genotoxic in a battery of in vitro assays (Ames mutation test in Salmonella, mutation test in L5178Y mouse lymphoma cells, and chromosome aberration assay in V79 Chinese hamster cells). Everolimus was not genotoxic in an in vivo mouse bone marrow micronucleus test at doses up to 500 mg/kg/day (1500 mg/m^2/day, approximately 255-fold the recommended dose of AFINITOR 10 mg orally once daily, and approximately 200-fold the median dose administered to patients with TSC-associated SEGA and TSC-associated partial-onset seizures, based on the BSA), administered as 2 doses, 24 hours apart.

Based on non-clinical findings, everolimus tablets for oral suspension may impair male fertility. In a 13-week male fertility study in rats, testicular morphology was affected at doses of 0.5 mg/kg and above. Sperm motility, sperm count, and plasma testosterone levels were diminished in rats treated with 5 mg/kg. The exposures at these doses (52 ng•hr/mL and 414 ng•hr/mL, respectively) were within the range of human exposure at the recommended dose of AFINITOR 10 mg orally once daily (560 ng•hr/mL) and resulted in infertility in the rats at 5 mg/kg. Effects on male fertility occurred at AUC0-24h values 10% to 81% lower than human exposure at the recommended dose of AFINITOR 10 mg orally once daily. After a 10-13 week non-treatment period, the fertility index increased from zero (infertility) to 60%.

Oral doses of everolimus in female rats at doses ≥ 0.1 mg/kg (approximately 4% the human exposure based on AUC at the recommended dose of AFINITOR 10 mg orally once daily) resulted in increased incidence of pre-implantation loss, suggesting that the drug may reduce female fertility.

13.2 Animal Toxicology and/or Pharmacology

In juvenile rat toxicity studies, dose-related delayed attainment of developmental landmarks, including delayed eye-opening, delayed reproductive development in males and females and increased latency time during the learning and memory phases were observed at doses as low as 0.15 mg/kg/day.

14 CLINICAL STUDIES

14.5 Tuberous Sclerosis Complex (TSC)-Associated Subependymal Giant Cell Astrocytoma (SEGA)

EXIST-1

A randomized (2:1), double-blind, placebo-controlled trial (EXIST-1, NCT00789828) of AFINITOR was conducted in 117 pediatric and adult patients with SEGA and TSC. Eligible patients had at least one SEGA lesion ≥ 1 cm in longest diameter on MRI based on local radiology assessment and one or more of the following: serial radiological evidence of SEGA growth, a new SEGA lesion ≥ 1 cm in longest diameter, or new or worsening hydrocephalus. Patients randomized to the treatment arm received AFINITOR at a starting dose of 4.5 mg/m^2 daily, with subsequent dose adjustments as needed to achieve and maintain everolimus trough concentrations of 5 to 15 ng/mL as tolerated. AFINITOR or matched placebo continued until disease progression or unacceptable toxicity. MRI scans for disease assessment were obtained at baseline, 12, 24, and 48 weeks, and annually thereafter.

The main efficacy outcome measure was SEGA response rate based on independent central radiology review. SEGA response was defined as a ≥ 50% reduction in the sum of SEGA volume relative to baseline, in the absence of unequivocal worsening of non-target SEGA lesions, a new SEGA lesion ≥ 1 cm, and new or worsening hydrocephalus. The primary analysis of SEGA response rate was limited to the blinded treatment period and conducted 6 months after the last patient was randomized. The analysis of SEGA response rate was stratified by use of enzyme-inducing antiepileptic drugs (EIAEDs) at randomization (yes vs. no).

Of the 117 patients enrolled, 78 were randomized to AFINITOR and 39 to placebo. The median age was 9.5 years (0.8 to 26 years); a total of 20 patients were < 3 years, 54 patients were 3 to < 12 years, 27 patients were 12 to < 18 years, and 16 patients were ≥ 18 years; 57% were male, and 93% were white. At baseline, 18% of patients were receiving EIAEDs. Based on central radiology review at baseline, 98% of patients had at least one SEGA lesion ≥ 1.0 cm in longest diameter, 79% had bilateral SEGAs, 43% had ≥ 2 target SEGA lesions, 26% had growth in or into the inferior surface of the ventricle, 9% had evidence of growth beyond the subependymal tissue adjacent to the ventricle, and 7% had radiographic evidence of hydrocephalus. The median values for the sum of all target SEGA lesions at baseline were 1.63 cm^3 (0.18 to 25.15 cm^3) and 1.30 cm^3 (0.32 to 9.75 cm^3) in the AFINITOR and placebo arms, respectively. Eight (7%) patients had prior SEGA-related surgery. The median duration of follow-up was 8.4 months (4.6 to 17.2 months) at the time of primary analysis.

The SEGA response rate was statistically significantly higher in AFINITOR-treated patients (Table 25). At the time of the primary analysis, all SEGA responses were ongoing and the median duration of response was 5.3 months (2.1 to 8.4 months).

With a median follow-up of 8.4 months, SEGA progression was detected in 15.4% of the 39 patients randomized to receive placebo and none of the 78 patients randomized to receive AFINITOR. No patient in either treatment arm required surgical intervention.

Table 25: Subependymal Giant Cell Astrocytoma Response Rate in TSC-Associated SEGA in EXIST-1
 | AFINITOR; N = 78 | Placebo; N = 39 | p-value
Primary analysis
SEGA response ratea- (%) | 35 | 0 | < 0.0001
95% CI | 24, 46 | 0, 9
aPer independent central radiology review.

Patients randomized to placebo were permitted to receive AFINITOR at the time of SEGA progression or after the primary analysis, whichever occurred first. After the primary analysis, patients treated with AFINITOR underwent additional follow-up MRI scans to assess tumor status until discontinuation of treatment or completion of 4 years of follow-up after the last patient was randomized. A total of 111 patients (78 patients randomized to AFINITOR and 33 patients randomized to placebo) received at least one dose of AFINITOR. Median duration of AFINITOR treatment and follow-up was 3.9 years (0.2 to 4.9 years).

By four years after the last patient was enrolled, 58% of the 111 patients treated with AFINITOR had a ≥ 50% reduction in SEGA volume relative to baseline, including 27 patients identified at the time of the primary analysis and 37 patients with a SEGA response after the primary analysis. The median time to SEGA response was 5.3 months (2.5 to 33.1 months). Twelve percent of the 111 patients treated with AFINITOR had documented disease progression by the end of the follow-up period and no patient required surgical intervention for SEGA during the study.

Study 2485

Study 2485 (NCT00411619) was an open-label, single-arm trial conducted to evaluate the antitumor activity of AFINITOR 3 mg/m^2/orally once daily in patients with SEGA and TSC. Serial radiological evidence of SEGA growth was required for entry. Tumor assessments were performed every 6 months for 60 months after the last patient was enrolled or disease progression, whichever occurred earlier. The major efficacy outcome measure was the reduction in volume of the largest SEGA lesion with 6 months of treatment, as assessed via independent central radiology review. Progression was defined as an increase in volume of the largest SEGA lesion over baseline that was ≥ 25% over the nadir observed on study.

A total of 28 patients received AFINITOR for a median duration of 5.7 years (5 months to 6.9 years); 82% of the 28 patients remained on AFINITOR for at least 5 years. The median age was 11 years (3 to 34 years), 61% male, 86% white.

At the primary analysis, 32% of the 28 patients (95% CI: 16%, 52%) had an objective response at 6 months, defined as at least a 50% decrease in volume of the largest SEGA lesion. At the completion of the study, the median duration of durable response was 12 months (3 months to 6.3 years).

By 60 months after the last patient was enrolled, 11% of the 28 patients had documented disease progression. No patient developed a new SEGA lesion while on AFINITOR. Nine additional patients were identified as having a ≥ 50% volumetric reduction in their largest SEGA lesion between 1 to 4 years after initiating AFINITOR, including 3 patients who had surgical resection with subsequent regrowth prior to receiving AFINITOR.

14.6 Tuberous Sclerosis Complex (TSC)-Associated Partial-Onset Seizures

The efficacy of everolimus tablets for oral suspension as an adjunctive anti-epileptic drug (AED) was evaluated in a randomized, double-blind, multicenter, placebo-controlled study conducted in patients with TSC-associated partial-onset seizures (EXIST-3, NCT01713946). Patients with a history of inadequate control of partial-onset seizures despite treatment with ≥ 2 sequential AED regimens were randomized to receive placebo or everolimus tablets for oral suspension once daily at a dose to achieve a low trough (LT) level (3-7 ng/mL) or a high trough (HT) level (9-15 ng/mL). Randomization was stratified by age group (1 to < 6, 6 to < 12, 12 to < 18, ≥ 18 years). The study consisted of 3 phases: an 8-week Baseline observation phase; an 18-week double-blind, placebo-controlled Core phase (6-week titration period and a 12-week maintenance period), and an Extension phase of ≥ 48 weeks. Patients were required to have a diagnosis of TSC per the modified Gomez criteria, and ≥ 16 partial-onset seizures during the Baseline phase while receiving a stable dose of 1 to 3 concomitant AEDs. The starting doses for everolimus tablets for oral suspension in the Core phase ranged from 3 to 6 mg/m^2 orally once daily, depending on age, in patients not receiving concomitant CYP3A4/P-gp inducers and from 5 to 9 mg/m^2 orally once daily, depending on age, in patients receiving concomitant CYP3A4/P-gp inducers. During the 6-week titration period, everolimus trough levels were assessed every 2 weeks and up to 3 dose adjustments were allowed to attempt to reach the targeted everolimus trough concentration range.

The major efficacy outcome measure was the percentage reduction in seizure frequency from the Baseline phase, during the maintenance period of the Core phase. Additional efficacy outcome measures included response rate, defined as at least a 50% reduction in seizure frequency from the Baseline phase during the maintenance period of the Core phase, and seizure freedom rate during the maintenance period of the Core phase.

A total of 366 patients were randomized to everolimus tablets for oral suspension LT (n = 117), everolimus tablets for oral suspension HT (n = 130) or placebo (n = 119). Median age was 10.1 years (2.2 to 56 years); 28% of patients were < 6 years, 31% were 6 to < 12 years, 22% were 12 to < 18 years, and 18% were ≥ 18 years). The majority were white (65%) and male (52%). The most common major features of TSC were cortical tubers (92%), hypomelanotic macules (84%), and subependymal nodules (83%). While 17% of the patients had SEGA, 42% had renal angiomyolipoma, and 9% had both SEGA and renal angiomyolipoma; no patients were receiving treatment with everolimus tablets for oral suspension for these manifestations of TSC. During the Baseline phase, 65% of patients had complex partial seizures, 52% had secondarily generalized seizures, 19% had simple partial seizures, and 2% had generalized onset seizures. The median seizure frequency per week during the Baseline phase was 9.4 for all patients and 47% of patients were receiving 3 AEDs during the Baseline phase. The efficacy results are summarized in Table 26.

Table 26: Percentage Reduction in Seizure Frequency and Response Rate in TSC-Associated Partial-Onset Seizures in EXIST-3

 | Everolimus Tablets for Oral Suspension |  | Placebo
 | Target of; 3-7 ng/mL; N = 117 | Target of; 9-15 ng/mL; N = 130
 | Target of; 3-7 ng/mL; N = 117 | Target of; 9-15 ng/mL; N = 130 | N = 119
Seizures per week
Median at Baseline (Min, Max) | 8.6 (1.4, 192.9) | 9.5 (0.3, 218.4) | 10.5 (1.3, 231.7)
Median at Core phasea (Min, Max) | 6.8 (0.0, 193.5) | 4.9 (0.0, 133.7) | 8.5 (0.0, 217.7)
Percentage reduction from Baseline to Core phase (Maintenancea)
Median | 29.3 | 39.6 | 14.9
95% CIb | 18.8, 41.9 | 35.0, 48.7 | 0.1, 21.7
p-valuec | 0.003 | < 0.001
Response rate
Responders, n (%) | 28.2 | 40 | 15.1
95% CId | 20.3, 37.3 | 31.5, 49.0 | 9.2, 22.8
aIf patient discontinued before starting the Maintenance period, then the Titration period is used.
b95% CI of the median based on bootstrap percentiles.
cp-values were for superiority vs. placebo, and obtained from rank ANCOVA with Baseline seizure frequency as covariate, stratified by age subgroup.
dExact 95% CI obtained using Clopper-Pearson method.

15 REFERENCES

1. OSHA Hazardous Drugs. OSHA. http://www.osha.gov/SLTC/hazardousdrugs/index.html.

16 HOW SUPPLIED/STORAGE AND HANDLING

Everolimus tablets for oral suspension

2 mg tablets: White to off white, round shaped, flat faced bevelled edged tablets debossed with "E2" on one side and plain on other side and free from physical defects.

HDPE Bottles of 28’s Count ---------------------------------- NDC 70377-090-11

Blisters of 28 tablets (Desiccant Embedded Alu-Alu Blister pack) -- NDC 70377-090-23

Each carton contains 4 blister cards of 7 tablets each

3 mg tablets: White to off white, round shaped, flat faced bevelled edged tablets debossed with "E3" on one side and plain on other side and free from physical defects.:

HDPE Bottles of 28’s Count ---------------------------------NDC 70377-091-11

Blisters of 28 tablets (Desiccant Embedded Alu-Alu Blister pack) -- NDC 70377-091-23

Each carton contains 4 blister cards of 7 tablets each

5 mg tablets: White to off white, round shaped, flat faced bevelled edged tablets debossed with "E5" on one side and plain on other side and free from physical defects.:

HDPE Bottles of 28’s Count ---------------------------------NDC 70377-092-11

Blisters of 28 tablets (Desiccant Embedded Alu-Alu Blister pack) -- NDC 70377-092-23

Each carton contains 4 blister cards of 7 tablets each

Store at 20°C to 25°C (68°F to 77°F); excursions permitted between 15°C to 30°C (59°F to 86°F). See USP Controlled Room Temperature.

Store in the original container, protect from light and moisture.

Follow special handling and disposal procedures for anti-cancer pharmaceuticals.^1

17 PATIENT COUNSELING INFORMATION

Advise the patient to read the FDA-approved patient labeling (Patient Information and Instructions for Use).

Non-infectious Pneumonitis

Advise patients of the risk of developing non-infectious pneumonitis and to immediately report any new or worsening respiratory symptoms to their healthcare provider [see Warnings and Precautions (5.1)].

Infections

Advise patients that they are more susceptible to infections and that they should immediately report any signs or symptoms of infections to their healthcare provider [see Warnings and Precautions (5.2)].

Hypersensitivity Reactions

Advise patients of the risk of clinically significant hypersensitivity reactions and to promptly contact their healthcare provider or seek emergency care for signs of hypersensitivity reaction, including rash, itching, hives, difficulty breathing or swallowing, flushing, chest pain, or dizziness [see Contraindications (4), Warnings and Precautions (5.3)].

Angioedema with Concomitant Use of ACE Inhibitors

Advise patients to avoid ACE inhibitors and to promptly contact their healthcare provider or seek emergency care for signs or symptoms of angioedema [see Warnings and Precautions (5.4)].

Stomatitis

Advise patients of the risk of stomatitis and to use alcohol-free mouthwashes during treatment [see Warnings and Precautions (5.5)].

Renal Impairment

Advise patients of the risk of developing kidney failure and the need to monitor their kidney function periodically during treatment [see Warnings and Precautions (5.6)].

Risk of Impaired Wound Healing

Advise patients that everolimus tablets for oral suspension may impair wound healing. Advise patients to inform their healthcare provider of any planned surgical procedure [see Warnings and Precautions (5.7)].

Metabolic Disorders

Advise patients of the risk of metabolic disorders and the need to monitor glucose and lipids periodically during therapy [see Warnings and Precautions (5.9)].

Myelosuppression

Advise patients of the risk of myelosuppression and the need to monitor CBCs periodically during therapy [see Warnings and Precautions (5.10)].

Risk of Infection or Reduced Immune Response With Vaccination

Advise patients to avoid the use of live vaccines and close contact with those who have received live vaccines [see Warnings and Precautions (5.11)].

Embryo-Fetal Toxicity

Advise females of reproductive potential of the potential risk to a fetus. Advise females of reproductive potential to use effective contraception during treatment and for 8 weeks after the last dose. Advise patients to inform their healthcare provider of a known or suspected pregnancy. Advise males with female partners of reproductive potential to use effective contraception during treatment and for 4 weeks after the last dose [see Warnings and Precautions (5.13), Use in Specific Populations (8.1, 8.3)].

Radiation Sensitization and Radiation Recall

Radiation sensitization and recall can occur in patients treated with radiation prior to, during, or subsequent to everolimus tablets for oral suspension treatment. Advise patients to inform their healthcare provider if they have had or are planning to receive radiation therapy [see Warnings and Precautions (5.12)].

Lactation

Advise women not to breastfeed during treatment with everolimus tablets for oral suspension and for 2 weeks after the last dose [see Use in Specific Populations (8.2)].

Infertility

Advise males and females of reproductive potential of the potential risk for impaired fertility [see Use in Specific Populations (8.3)].

All brand names listed are the registered trademarks of their respective owners and are not trademarks of Biocon Pharma Limited.

Manufactured by:

Biocon Pharma Limited

Bengaluru, India – 560099

Manufactured for:

Biocon Pharma Inc.,

Iselin, New Jersey, 08830-3009

United States of America

PATIENT INFORMATION

Everolimus Tablets for Oral Suspension

(e” ver oh’ li mus)

Read this Patient Information leaflet that comes with everolimus tablets for oral suspension before you start taking it and each time you get a refill. There may be new information. This information does not take the place of talking to your healthcare provider about your medical condition or treatment.

What is the most important information I should know about everolimus tablets for oral suspension?

Everolimus tablets for oral suspension can cause serious side effects, including:

1. You may develop lung or breathing problems. In some people lung or breathing problems may be severe and can lead to death. Tell your healthcare provider right away if you have any of these symptoms:

- New or worsening cough
- Shortness of breath
- Chest pain
- Difficulty breathing or wheezing

2. You may be more likely to develop an infection, such as pneumonia, or a bacterial, fungal or viral infection. Viral infections may include active hepatitis B in people who have had hepatitis B in the past (reactivation). In some people (including adults and children) these infections may be severe and can lead to death. You may need to be treated as soon as possible.

Tell your healthcare provider right away if you have a temperature of 100.5˚F or above, chills, or do not feel well.

Symptoms of hepatitis B or infection may include the following:

• Fever • Loss of appetite

• Chills • Nausea

• Skin rash • Pale stools or dark urine

• Joint pain and swelling • Yellowing of the skin

• Tiredness • Pain in the upper right side of the stomach

3. Severe allergic reactions. Call your healthcare provider or get medical help right away if you get signs and symptoms of a severe allergic reaction, including: rash, itching, hives, flushing, trouble breathing or swallowing, chest pain or dizziness.

4. Possible increased risk for a type of allergic reaction called angioedema, in people who take an Angiotensin-Converting Enzyme (ACE) inhibitor medicine during treatment with everolimus tablets for oral suspension. Talk with your healthcare provider before taking everolimus tablets for oral suspension if you are not sure if you take an ACE inhibitor medicine. Get medical help right away if you have trouble breathing or develop swelling of your tongue, mouth, or throat during treatment with everolimus tablets for oral suspension.

5. Mouth ulcers and sores. Mouth ulcers and sores are common during treatment with everolimus tablets for oral suspension but can also be severe. When you start treatment with everolimus tablets for oral suspension, your healthcare provider may tell you to also start a prescription mouthwash to reduce the likelihood of getting mouth ulcers or sores and to reduce their severity. Follow your healthcare provider’s instructions on how to use this prescription mouthwash. If you develop pain, discomfort, or open sores in your mouth, tell your healthcare provider. Your healthcare provider may tell you to restart this mouthwash or to use a special mouthwash or mouth gel that does not contain alcohol, peroxide, iodine, or thyme.

6. You may develop kidney failure. In some people this may be severe and can lead to death. Your healthcare provider should do tests to check your kidney function before and during your treatment with everolimus tablets for oral suspension.

If you have any of the serious side effects listed above, you may need to stop taking everolimus tablets for oral suspension for a while or use a lower dose. Follow your healthcare provider’s instructions.

What are everolimus tablets for oral suspension?

Everolimus tablets for oral suspension are a prescription medicine used to treat:

- adults and children 1 year of age and older with a genetic condition called tuberous sclerosis complex (TSC) who have a brain tumor called subependymal giant cell astrocytoma (SEGA) when the tumor cannot be removed completely by surgery.
- adults and children 2 years of age and older with a genetic condition called tuberous sclerosis complex (TSC) who have certain types of seizures (epilepsy), as an added treatment to other antiepileptic medicines.

Do not take everolimus tablets for oral suspension if you have had a severe allergic reaction to everolimus.

Talk to your healthcare provider before taking this medicine if you are allergic to:

- a medicine that contains sirolimus
- a medicine that contains temsirolimus

Ask your healthcare provider if you do not know.

Before taking everolimus tablets for oral suspension, tell your healthcare provider about all of your medical conditions, including if you:

- Have or have had kidney problems
- Have or have had liver problems
- Have diabetes or high blood sugar
- Have high blood cholesterol levels
- Have any infections
- Previously had hepatitis B
- Are scheduled to receive any vaccinations. You should not receive a “live vaccine” or be around people who have recently received a “live vaccine” during your treatment with everolimus tablets for oral suspension. If you are not sure about the type of immunization or vaccine, ask your healthcare provider. For children with TSC and SEGA or certain types of seizures, work with your healthcare provider to complete the recommended childhood series of vaccines before your child starts treatment with everolimus tablets for oral suspension.
- Are pregnant, can become pregnant, or have a partner who can become pregnant. Everolimus tablets for oral suspension can cause harm to your unborn baby.

Females who are able to become pregnant:

- Your healthcare provider will give you a pregnancy test before you start treatment with everolimus tablets for oral suspension.
- You should use effective birth control during treatment and for 8 weeks after your last dose of everolimus tablets for oral suspension.

Males with a female partner, you should use effective birth control during treatment and for 4 weeks after your last dose of everolimus tablets for oral suspension.

Talk to your healthcare provider about birth control methods that may be right for you during this time. If you become pregnant or think you are pregnant, tell your healthcare provider right away.

- Are breastfeeding or plan to breastfeed. It is not known if everolimus passes into your breast milk. Do not breastfeed during treatment and for 2 weeks after your last dose of everolimus tablets for oral suspension.
- Are planning to have surgery or if you have had a recent surgery. You should stop taking everolimus tablets for oral suspension at least 1 week before planned surgery. See “What are the possible side effects of everolimus tablets for oral suspension?”
- Have received radiation therapy or are planning to receive radiation therapy in the future. See “What are the possible side effects of everolimus tablets for oral suspension?”

Tell your healthcare provider about all of the medicines you take, including prescription and over-the-counter medicines, vitamins, and herbal supplements.

Everolimus tablets for oral suspension may affect the way other medicines work, and other medicines can affect how everolimus tablets for oral suspension work. Taking everolimus tablets for oral suspension with other medicines can cause serious side effects.

Know the medicines you take. Keep a list of them and show it to your healthcare provider and pharmacist when you get a new medicine. Especially tell your healthcare provider if you take:

- St. John’s Wort (Hypericum perforatum)
- Medicine for:

- Fungal infections
- Bacterial infections
- Tuberculosis
- Seizures
- HIV-AIDS
- Heart conditions or high blood pressure

- Medicines that weaken your immune system (your body’s ability to fight infections and other problems)

Ask your healthcare provider or pharmacist if you are not sure if your medicine is one of those taken for the conditions listed above. If you are taking any medicines for the conditions listed above, your healthcare provider might need to prescribe a different medicine or your dose of everolimus tablets for oral suspension may need to be changed. You should also tell your healthcare provider before you start taking any new medicine.

How should I take everolimus tablets for oral suspension?

- Your healthcare provider will prescribe the dose of everolimus tablets for oral suspension that is right for you.
- Take everolimus tablets for oral suspension exactly as your healthcare provider tells you to.
- Your healthcare provider may change your dose of everolimus tablets for oral suspension or tell you to temporarily interrupt dosing, if needed.
- Take only AFINITOR or everolimus tablets for oral suspension. Do not mix AFINITOR and everolimus tablets for oral suspension together.
- Use scissors to open the blister pack. For HDPE bottle pack, push and twist the cap to open the bottle.
- Take everolimus tablets for oral suspension 1 time each day at about the same time.
- Take everolimus tablets for oral suspension the same way each time, either with food or without food.
- If you take too many everolimus tablets for oral suspension, contact your healthcare provider or go to the nearest hospital emergency room right away. Take the pack of everolimus tablets for oral suspension with you.
- If you miss a dose of everolimus tablets for oral suspension, you may take it if it is less than 6 hours after the time you normally take it. If it is more than 6 hours after you normally take your everolimus tablets for oral suspension, skip the dose for that day. The next day, take everolimus tablets for oral suspension at your usual time. Do not take 2 doses to make up for a missed dose. If you are not sure about what to do, call your healthcare provider.
- You should have blood tests before you start everolimus tablets for oral suspension and as needed during your treatment. These will include tests to check your blood cell count, kidney and liver function, cholesterol, and blood sugar levels.
- If you take everolimus tablets for oral suspension to treat SEGA or to treat certain types of seizures with TSC, you will also need to have blood tests regularly to measure how much medicine is in your blood. This will help your healthcare provider decide how many everolimus tablets for oral suspension you need to take.

Everolimus tablets for oral suspension:

- If your healthcare provider prescribes everolimus tablets for oral suspension for you, see the “Instructions for Use” that comes with your medicine for instructions on how to prepare and take your dose.
- Each dose of everolimus tablets for oral suspension must be prepared as a suspension before it is given.
- Everolimus tablets for oral suspension can cause harm to an unborn baby. When possible, the suspension should be prepared by an adult who is not pregnant or planning to become pregnant.
- Wear gloves to avoid possible contact with everolimus when preparing suspensions of everolimus tablets for oral suspension for another person.

What should I avoid while taking everolimus tablets for oral suspension?

You should not drink grapefruit juice or eat grapefruit during your treatment with everolimus tablets for oral suspension. It may make the amount of everolimus in your blood increase to a harmful level

What are the possible side effects of everolimus tablets for oral suspension?

Everolimus tablets for oral suspension can cause serious side effects, including:

- See “What is the most important information I should know about everolimus tablets for oral suspension?” for more information.
- Risk of wound healing problems. Wounds may not heal properly during everolimus tablets for oral suspension treatment. Tell your healthcare provider if you plan to have any surgery before starting or during treatment with everolimus tablets for oral suspension

- You should stop taking everolimus tablets for oral suspension at least 1 week before planned surgery.
- Your healthcare provider should tell you when you may start taking everolimus tablets for oral suspension again after surgery.

- Increased blood sugar and fat (cholesterol and triglyceride) levels in the blood. Your healthcare provider should do blood tests to check your fasting blood sugar, cholesterol, and triglyceride levels in the blood before you start and during treatment with everolimus tablets for oral suspension.
- Decreased blood cell counts. Everolimus tablets for oral suspension can cause you to have decreased red blood cells, white blood cells, and platelets. Your healthcare provider should do blood tests to check your blood cell counts before you start and during treatment with everolimus tablets for oral suspension.
- Worsening side effects from radiation treatment, that can sometimes be severe. Tell your healthcare provider if you have had or are planning to receive radiation therapy.

The most common side effects of everolimus tablets for oral suspension in people who have SEGA or certain types of seizures with TSC include respiratory tract infections.

Other side effects that may occur with everolimus tablets for oral suspension:

- Absence of menstrual periods (menstruation). You may miss 1 or more menstrual periods. Tell your healthcare provider if this happens.
- Everolimus tablets for oral suspension may affect fertility in females and may affect your ability to become pregnant. Talk to your healthcare provider if this is a concern for you.
- Everolimus tablets for oral suspension may affect fertility in males and may affect your ability to father a child. Talk to your healthcare provider if this is a concern for you.

Tell your healthcare provider if you have any side effect that bothers you or does not go away.

These are not all the possible side effects of everolimus tablets for oral suspension. For more information, ask your healthcare provider or pharmacist.

Call your doctor for medical advice about side effects. You may report side effects to FDA at 1-800-FDA-1088.

How should I store everolimus tablets for oral suspension?

- Store everolimus tablets for oral suspension at room temperature, between 68°F to 77°F (20°C to 25°C).
- Keep everolimus tablets for oral suspension in the pack it comes in.
- Open the blister pack just before taking everolimus tablets for oral suspension.
- Keep everolimus tablets for oral suspension dry and away from light.
- Do not use everolimus tablets for oral suspension that is out of date or no longer needed.

Keep everolimus tablets for oral suspension and all medicines out of the reach of children.

General information about the safe and effective use of everolimus tablets for oral suspension. Medicines are sometimes prescribed for purposes other than those listed in a Patient Information leaflet. Do not use everolimus tablets for oral suspension for a condition for which it was not prescribed. Do not give everolimus tablets for oral suspension to other people, even if they have the same problem you have. It may harm them. This leaflet summarizes the most important information about everolimus tablets for oral suspension. If you would like more information, talk with your healthcare provider. You can ask your healthcare provider or pharmacist for information written for healthcare professionals.

For more information, call Biocon Pharma Inc., at 1-866-924-6266.

What are the ingredients in everolimus tablets for oral suspension?

Active ingredient: everolimus.

Inactive ingredients: butylated hydroxytoluene, colloidal silicon dioxide, crospovidone, hypromellose, magnesium stearate, mannitol, and microcrystalline cellulose.

Manufactured by:

Biocon Pharma Limited

Bengaluru, India - 560099

Manufactured for:

Biocon Pharma Inc.,

Iselin, New Jersey, 08830-3009

United States of America

All brand names listed are the registered trademarks of their respective owners and are not trademarks of Biocon Pharma Limited.

This Patient Information has been approved by the U.S. Food and Drug Administration. Revised: 10/2025

PATIENT INFORMATION

Instructions For Use

Everolimus Tablets For Oral Suspension

(e” ver oh’ li mus)

Read these Instructions for Use for everolimus tablets for oral suspension before you start taking it and each time you get a refill. There may be new information. This information does not take the place of talking to your healthcare provider about your medical condition or treatment.

Important Information:

- Take everolimus tablets for oral suspension as a suspension only. Everolimus tablets for oral suspension is prepared as a suspension of undissolved medicine that is mixed with water, and then it is taken by mouth. Do not chew, crush, or swallow everolimus tablets for oral suspension whole.
- Everolimus tablets for oral suspension can cause harm to an unborn baby. When possible, the suspension should be prepared by an adult who is not pregnant or planning to become pregnant.
- Keep everolimus tablets for oral suspension and the prepared suspension out of the reach of children.
- Anyone who prepares suspensions of everolimus tablets for oral suspension for another person should wear gloves to avoid possible contact with the drug.
- Only use water with everolimus tablets for oral suspension to prepare the suspension. Do not prepare the suspension with juice or any other liquids.
- The suspension must be given right away. If you do not give the dose within 60 minutes after it has been prepared, throw away the dose and prepare a new dose of everolimus tablets for oral suspension.
- Before starting to prepare the suspension, collect all of the supplies that you will need to prepare and take the suspension. Do not use any of these supplies for purposes other than preparing and taking the everolimus tablets for oral suspension.

Supplies needed to prepare the suspension in an oral syringe:

- Bottle or blister card with everolimus tablets for oral suspension
- Scissors to open the blister card
- Disposable gloves (for one time use)
- 2 clean drinking glasses
- Approximately 30 mL of water
- 10 mL oral syringe (for one time use) (see Figure A)
- Paper towels

Figure A

Supplies needed to prepare the suspension in a small drinking glass:

- Bottle or blister card with everolimus tablets for oral suspension.
- Scissors to open the blister card.
- Disposable gloves (for one time use)
- 30 mL dose cup for measuring water (you can ask your pharmacist for this)
- 1 clean drinking glass (maximum size 100 mL)
- Water to prepare the suspension
- Spoon for stirring
- Paper towels

Preparing a dose of everolimus tablets for oral suspension using an oral syringe:

Step 1: Prepare a clean, flat work surface that is away from where you prepare and eat food. Place a clean paper towel on the work surface. Place the needed supplies on the paper towel.

Step 2: Wash and dry your hands well before preparing the medicine (see Figure B).

Figure B

Step 3: If preparing the everolimus tablets for oral suspension for another person, put on disposable gloves (see Figure C).

Figure C

Step 4: Take a 10 mL oral syringe and pull back on the plunger. Remove the plunger from the barrel of the syringe (see Figure D).

Figure D

Step 5: Use scissors to open the blister card along the dotted line and for HDPE bottle pack, push and twist the cap to open the bottle (see Figure E) and remove the prescribed number of everolimus tablets for oral suspension from the blister card or bottle. Place them into the barrel of the oral syringe (see Figure F).

Figure E

Figure F

- Doses of up to 10 mg can be prepared with the oral syringe. If your total prescribed dose is more than 10 mg, you will need to split the dose. Follow steps 4 through 17 for the first half of the dose. Then repeat steps 4 through 17 for the second half of the dose. Do not prepare a dose of more than 10 mg in one syringe. Ask your pharmacist or healthcare provider if you are not sure what to do.

Step 6: Re-insert the plunger into the barrel of the oral syringe (see Figure G) and push the plunger in until it comes into contact with the everolimus tablets for oral suspension (see Figure H).

Figure G

Figure H

Step 7: Fill a small drinking glass with about 30 mL of water. Insert the tip of the oral syringe into the water. Then slowly pull back on the plunger until the syringe is about half full of water and all the tablets are covered by water (see Figure I).

Figure I

Step 8: Hold the oral syringe with the tip pointing up. Pull back on the plunger to draw back about 4 mL of air (see Figure J).

Figure J

Step 9: Place the filled oral syringe in the clean, empty glass with the tip pointing up. Wait 3 minutes to allow everolimus tablets for oral suspension to break apart (see Figure K).

Figure K

Step 10: Slowly turn the oral syringe up and down five times just before giving the dose (see Figure L). Do not shake the syringe.

Figure L

Step 11: Hold the oral syringe in an upright position (with the tip up). Carefully remove most of the air by pushing up gently on the plunger (see Figure M).

Figure M

Step 12: Give the full contents of the oral syringe slowly and gently into the mouth right away, within 60 minutes of preparing it (see Figure N). Carefully remove the syringe from the mouth. Continue with steps 13 through 17 to make sure that the entire dose of medicine is given.

Figure N

Step 13: Insert the tip of the oral syringe into the drinking glass that is filled with water, and pull up about 5 mL of water by slowly pulling back on the plunger (see Figure O).

Figure O

Step 14: Hold the oral syringe with the tip pointing up and use the plunger to draw back about 4 mL of air (see Figure P).

Figure P

Step 15: With the tip of the syringe still pointing up, swirl the contents by gently rotating the syringe in a circular motion (see Figure Q).

Figure Q

Step 16: Hold the oral syringe in an upright position (with the tip up). Carefully remove most of the air by pushing up gently on the plunger (see Figure R).

Figure R

Step 17: Give the full contents of the oral syringe slowly and gently into the mouth by pushing on the plunger (see Figure S). Carefully remove the syringe from the mouth.

Figure S

If the total prescribed dose is more than 10 mg, repeat steps 4 through 17 to finish giving the dose.

Step 18: Throw away the oral syringe, paper towel, and used gloves in your household trash.

Step 19: Wash your hands.

Preparing a dose of everolimus tablets for oral suspension using a small drinking glass:

Step 1: Prepare a clean, flat work surface that is away from where you prepare and eat food. Place a clean paper towel on the work surface. Place the needed supplies on the paper towel.

Step 2: Wash and dry your hands before preparing the medicine (see Figure T).

Figure T

Step 3: If preparing the everolimus tablets for oral suspension for another person, put on disposable gloves (see Figure U).

Figure U

Step 4: Add about 25 mL of water to the 30 mL dose cup. The amount of water added does not need to be exact (see Figure V).

Figure V

Step 5: Pour the water from the dose cup into a small drinking glass (maximum size 100 mL) (see Figure W).

Figure W

- Doses up to 10 mg can be prepared in the small drinking glass. If your total prescribed dose is more than 10 mg, you will need to split the dose. Follow steps 4 through 10 for the first half of the dose. Then repeat steps 4 through 10 for the second half of the dose. Ask your pharmacist or healthcare provider if you are not sure what to do.

Step 6: Use scissors to open the blister card along the dotted line and for HDPE bottle pack, push and twist the cap to open the bottle (see Figure X) and remove the prescribed number of everolimus tablets for oral suspension from the blister card or bottle.

Figure X

Step 7: Add the prescribed number of everolimus tablets for oral suspension into the water (see Figure Y).

Figure Y

Step 8: Wait 3 minutes to allow everolimus tablets for oral suspension to break apart (see Figure Z).

Figure Z

Step 9: Gently stir the contents of the glass with a spoon and place the spoon back on the paper towel (see Figure AA). Drink the full amount of the suspension right away, within 60 minutes of preparing it (see Figure BB).

Figure AA

Figure BB

Step 10: Refill the glass with the same amount of water (about 25 mL). Stir the contents with the same spoon and place the spoon back on the paper towel (see Figure CC). Drink the full amount right away so that you take any remaining medicine (see Figure DD).

Figure CC

Figure DD

If your total prescribed dose is more than 10 mg, repeat steps 4 through 10 to finish taking your dose.

Step 11: Wash the glass and the spoon thoroughly with water. Wipe the glass and spoon with a clean paper towel and store them in a dry and clean place until your next dose of everolimus tablets for oral suspension (see Figure EE).

Figure EE

Step 12: Throw away the used paper towel and gloves in your household trash.

Step 13: Wash your hands.

How should I store everolimus tablets for oral suspension?

- Store everolimus tablets for oral suspension at room temperature, between 68°F to 77°F (20°C to 25°C).
- Keep everolimus tablets for oral suspension in the pack it comes in.
- Open the blister pack just before taking everolimus tablets for oral suspension.
- Keep everolimus tablets for oral suspension dry and away from light.
- Do not use everolimus tablets for oral suspension that is out of date or no longer needed.

Keep everolimus tablets for oral suspension and all medicines out of the reach of children.

This Instructions for Use has been approved by the U.S. Food and Drug Administration.

Manufactured by:

Biocon Pharma Limited

Bengaluru, India - 560099

Manufactured for:

Biocon Pharma Inc.,

Iselin, New Jersey, 08830-3009

United States of America

Revised: 09/2024

PRINCIPAL DISPLAY PANEL - 2 mg Bottle Label

NDC 70377-090-11

Everolimus Tablets

for Oral Suspension

2 mg

TABLETS MUST BE DISPERSED IN WATER.

TABLETS MUST NOT BE SWALLOWED WHOLE, CHEWED OR CRUSHED.

Rx only

28 Tablets

for Oral Suspension

PRINCIPAL DISPLAY PANEL - 3 mg Bottle Label

NDC 70377-091-11

Everolimus Tablets

for Oral Suspension

3 mg

TABLETS MUST BE DISPERSED IN WATER.

TABLETS MUST NOT BE SWALLOWED WHOLE, CHEWED OR CRUSHED.

Rx only

28 Tablets

for Oral Suspension

PRINCIPAL DISPLAY PANEL - 5 mg Bottle Label

NDC 70377-092-11

Everolimus Tablets

for Oral Suspension

5 mg

TABLETS MUST BE DISPERSED IN WATER.

TABLETS MUST NOT BE SWALLOWED WHOLE, CHEWED OR CRUSHED.

Rx only

28 Tablets

for Oral Suspension

PRINCIPAL DISPLAY PANEL - 2 mg Pealable Foil Label

NDC 70377-090-23 Rx only

Everolimus tablet for oral suspension 2 mg

Store at 20°C to 25°C (68°F to 77°F); excursions permitted between 15°C to 30°C (59°F to 86°F) [see USP Controlled Room Temperature]. Store in the original container; protect from light and moisture.

PRINCIPAL DISPLAY PANEL - 3 mg Pealable Foil Label

NDC 70377-091-23 Rx only

Everolimus tablet for oral suspension 2 mg

Store at 20°C to 25°C (68°F to 77°F); excursions permitted between 15°C to 30°C (59°F to 86°F) [see USP Controlled Room Temperature]. Store in the original container; protect from light and moisture.

PRINCIPAL DISPLAY PANEL - 5mg Pealable Foil Label

NDC 70377-092-23 Rx only

Everolimus tablet for oral suspension 2 mg

Store at 20°C to 25°C (68°F to 77°F); excursions permitted between 15°C to 30°C (59°F to 86°F) [see USP Controlled Room Temperature]. Store in the original container; protect from light and moisture.

PRINCIPAL DISPLAY PANEL - 2 mg Desiflex Label

NDC 70377-090-23 Rx only

Everolimus tablet for oral suspension 2 mg

Store at 20°C to 25°C (68°F to 77°F); excursions permitted between 15°C to 30°C (59°F to 86°F) [see USP Controlled Room Temperature]. Store in the original container; protect from light and moisture.

PRINCIPAL DISPLAY PANEL - 5mg Desiflex Label

NDC 70377-092-23 Rx only

Everolimus tablet for oral suspension 2 mg

Store at 20°C to 25°C (68°F to 77°F); excursions permitted between 15°C to 30°C (59°F to 86°F) [see USP Controlled Room Temperature]. Store in the original container; protect from light and moisture.

PRINCIPAL DISPLAY PANEL - 3 mg Desiflex Label

NDC 70377-091-23 Rx only

Everolimus tablet for oral suspension 2 mg

Store at 20°C to 25°C (68°F to 77°F); excursions permitted between 15°C to 30°C (59°F to 86°F) [see USP Controlled Room Temperature]. Store in the original container; protect from light and moisture.